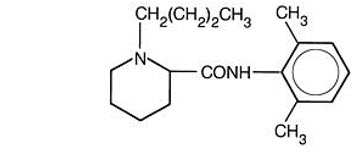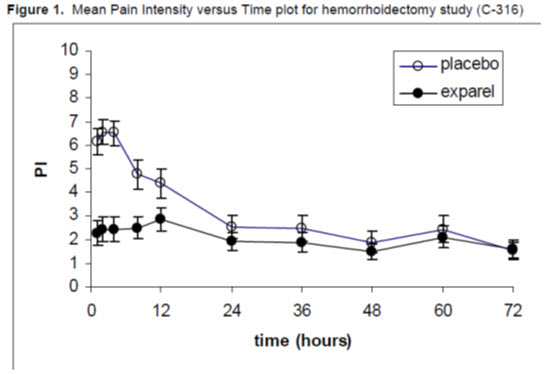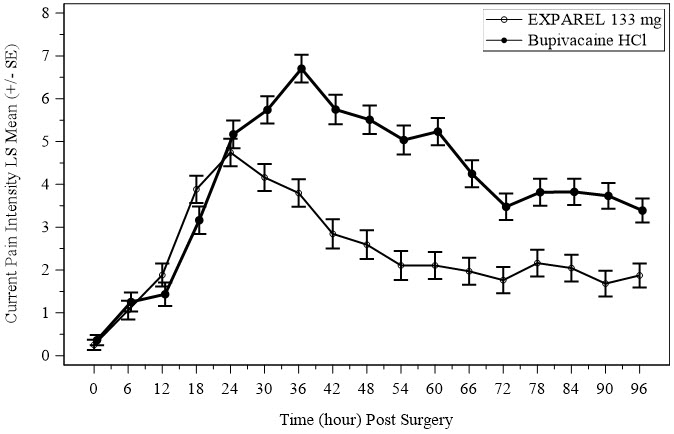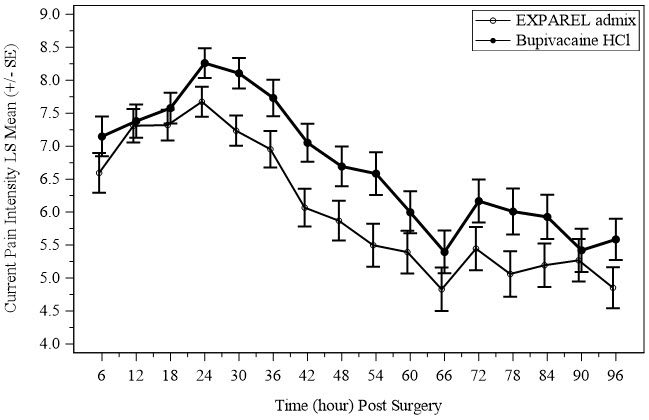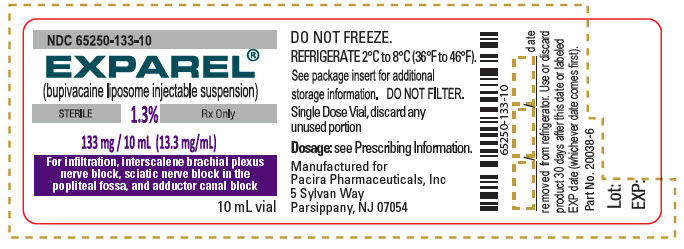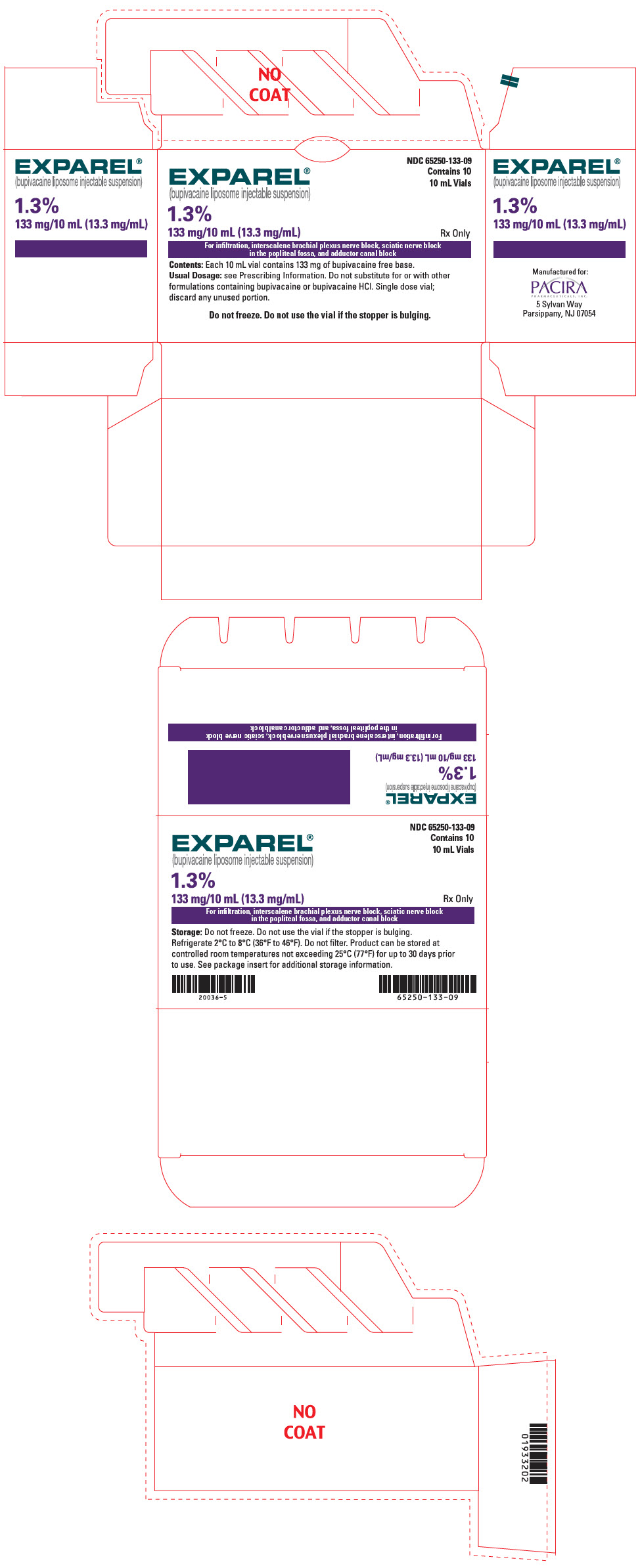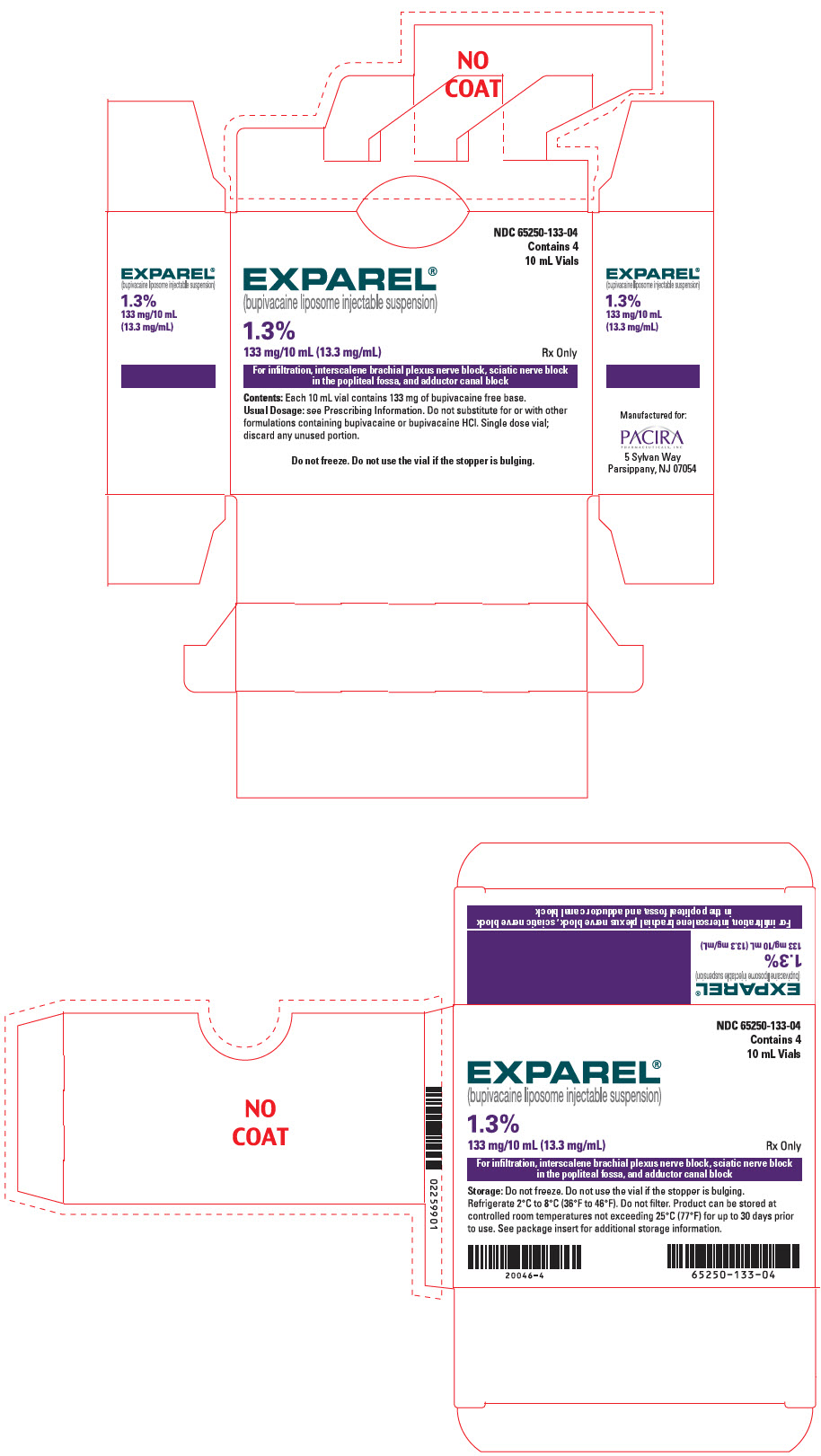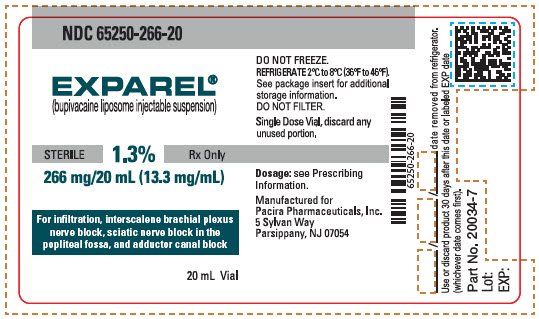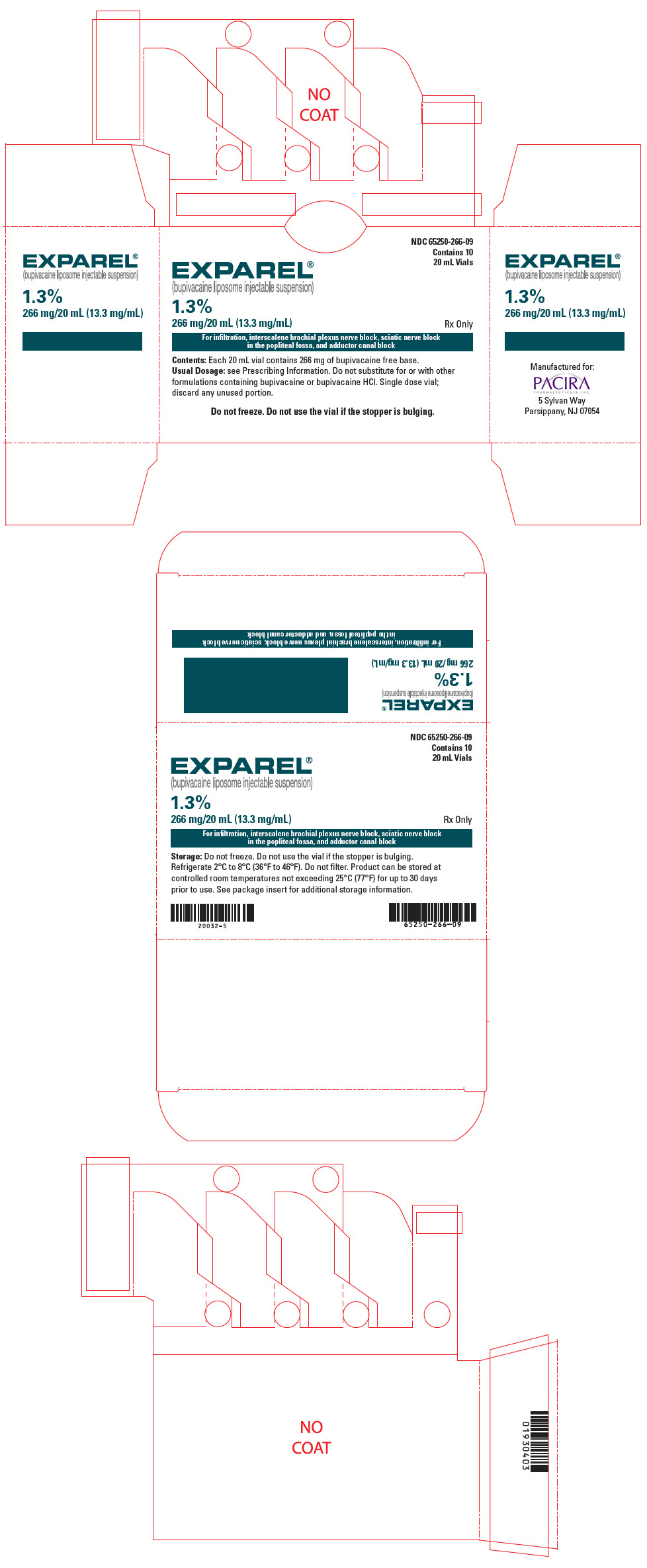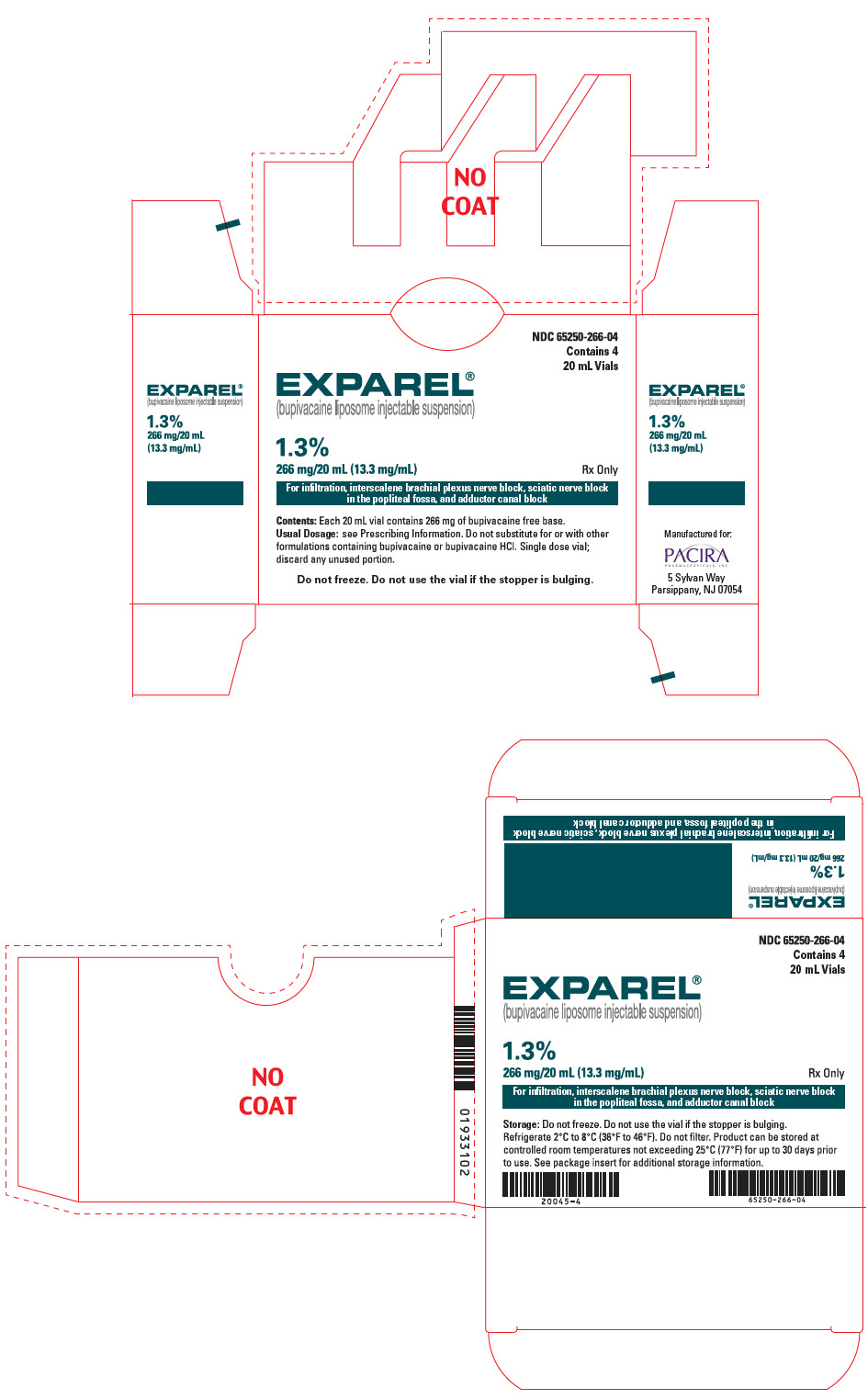 DRUG LABEL: EXPAREL
NDC: 65250-133 | Form: INJECTION, SUSPENSION, LIPOSOMAL
Manufacturer: Pacira Pharmaceuticals, Inc.
Category: prescription | Type: HUMAN PRESCRIPTION DRUG LABEL
Date: 20251212

ACTIVE INGREDIENTS: BUPIVACAINE 13.3 mg/1 mL

HIGHLIGHTS OF PRESCRIBING INFORMATION

These highlights do not include all the information needed to use EXPAREL® safely and effectively. See full prescribing information for EXPAREL.
EXPAREL (bupivacaine liposome injectable suspension), for infiltration or perineural use
Initial U.S. Approval: 1972

RECENT MAJOR CHANGES

Indications and Usage (1) | 11/ 2023
Dosage and Administration (2.2) | 11/2023

1 INDICATIONS AND USAGE

EXPAREL contains bupivacaine, an amide local anesthetic, and is indicated to produce postsurgical:

- Local analgesia via infiltration in patients aged 6 years and older (1).
- Regional analgesia via an interscalene brachial plexus nerve block in adults (1).
- Regional analgesia via a sciatic nerve block in the popliteal fossa in adults (1).
- Regional analgesia via an adductor canal block in adults (1).

Limitations of Use

The safety and effectiveness of EXPAREL have not been established to produce postsurgical regional analgesia via other nerve blocks besides an interscalene brachial plexus nerve block, a sciatic nerve block in the popliteal fossa, or an adductor canal block.

2 DOSAGE AND ADMINISTRATION

- EXPAREL is for single administration only (2.1).
- EXPAREL is not substitutable with other bupivacaine products even if the strength is the same. Therefore, it is not possible to convert a dose from other bupivacaine products to an EXPAREL dose and vice versa (2.1, 2.5).
- Do not dilute EXPAREL with water or other hypotonic solutions (2.1).
- The recommended dose of EXPAREL for:
  - Local infiltration in adults is up to a maximum dose of 266 mg. See Full Prescribing Information for guidance on dose selection (2.2).
  - Local infiltration in pediatric patients aged 6 to less than 17 years is 4 mg/kg, up to a maximum of 266 mg (2.2).
  - Interscalene brachial plexus nerve block in adults is 133 mg (2.3).
  - Sciatic nerve block in the popliteal fossa in adults is 133 mg (2.3).
  - Adductor canal block in adults is 133 mg (10 mL) admixed with 50 mg (10 mL) 0.5% bupivacaine HCl, for a total volume of 20 mL (2.3).
- For all these nerve blocks, administer additional analgesics, which may include other immediate-release local anesthetics, as appropriate (2.3).
- See Full Prescribing Information for important preparation and administration instructions and compatibility considerations (2.4, 2.5).

3 DOSAGE FORMS AND STRENGTHS

Injectable suspension:

1.3% (266 mg/20 mL) (13.3 mg/mL) in a single-dose vial (3)

1.3% (133 mg/10 mL) (13.3 mg/mL) in a single-dose vial (3)

4 CONTRAINDICATIONS

EXPAREL is contraindicated in obstetrical paracervical block anesthesia (4).

5 WARNINGS AND PRECAUTIONS

- Monitor cardiovascular status, neurological status, and vital signs during and after injection of EXPAREL (5.1).
- Because amide-type local anesthetics, such as bupivacaine, are metabolized by the liver, use EXPAREL cautiously in patients with hepatic disease. Patients with severe hepatic disease, because of their inability to metabolize local anesthetics normally, are at a greater risk of developing toxic plasma concentrations (5.1).
- Methemoglobinemia: Cases of methemoglobinemia have been reported in association with local anesthetic use (5.1).
- Avoid additional use of local anesthetics within 96 hours following administration of EXPAREL (5.2).

6 ADVERSE REACTIONS

Adverse reactions reported with an incidence greater than or equal to 10% following EXPAREL administration via:

- Infiltration in adults were nausea, constipation, and vomiting (6.1).
- Nerve block in adults were nausea, pyrexia, headache, and constipation (6.1).
- Infiltration in pediatric patients six to less than 17 years of age were nausea, vomiting, constipation, hypotension, anemia, muscle twitching, blurred vision, pruritus, and tachycardia (6.1).

To report SUSPECTED ADVERSE REACTIONS, contact Pacira Pharmaceuticals, Inc. at 1-855-RX-EXPAREL (1-855-793-9727) or FDA at 1-800-FDA-1088 or www.fda.gov/medwatch.

7 DRUG INTERACTIONS

- Lidocaine or other non-bupivacaine local anesthetics: Do not admix with EXPAREL. EXPAREL may be administered at least 20 minutes or more following local administration of lidocaine (7).
- Bupivacaine HCl: Do not exceed a milligram dose of bupivacaine HCl solution to EXPAREL of 1:2 when admixing, as this may impact the pharmacokinetics and/or physicochemical properties of the drugs (7).

8 USE IN SPECIFIC POPULATIONS

Pregnancy: May cause fetal harm (8.1).

FULL PRESCRIBING INFORMATION

1 INDICATIONS AND USAGE

EXPAREL is indicated to produce postsurgical:

- Local analgesia via infiltration in patients aged 6 years and older
- Regional analgesia via an interscalene brachial plexus nerve block in adults
- Regional analgesia via a sciatic nerve block in the popliteal fossa in adults
- Regional analgesia via an adductor canal block in adults

Limitations of Use

The safety and effectiveness of EXPAREL have not been established to produce postsurgical regional analgesia via other nerve blocks besides an interscalene brachial plexus nerve block, a sciatic nerve block in the popliteal fossa, or an adductor canal block.

2 DOSAGE AND ADMINISTRATION

2.1 Important Dose, Preparation, and Administration Instructions

- EXPAREL is for single administration only.
- EXPAREL is not substitutable with other bupivacaine products even if the strength is the same. Therefore, it is not possible to convert a dose from other bupivacaine products to an EXPAREL dose and vice versa.
- Do not dilute EXPAREL with water or other hypotonic agents, as it will result in disruption of the liposomal particles.
- Do not administer EXPAREL if it is suspected that the vial has been frozen or exposed to high temperature (greater than 40°C or 104°F) for an extended period.
- Inspect EXPAREL visually for particulate matter and discoloration prior to administration, whenever solution and container permit. Do not administer EXPAREL if the product is discolored.
- Do not heat or autoclave before use.
- Do not filter during administration.

2.2 Recommended Dose for Local Analgesia via Infiltration

Local Analgesia via Infiltration in Adults

The recommended dose of EXPAREL for local infiltration in adults is up to a maximum dose of 266 mg, and is based on the following factors:

- Size of the surgical site
- Volume required to cover the area
- Individual patient factors that may impact the safety of an amide local anesthetic

As general guidance in selecting the proper EXPAREL dose for local infiltration in adults, two examples are provided [see Clinical Studies (14.2)]. In adult patients undergoing:

- Bunionectomy, a total of 106 mg (8 mL) of EXPAREL was administered, with 7 mL infiltrated into the tissues surrounding the osteotomy, and 1 mL infiltrated into the subcutaneous tissue.
- Hemorrhoidectomy, a total of 266 mg (20 mL) of EXPAREL was diluted with 10 mL of saline, for a total of 30 mL, divided into six 5 mL aliquots, injected by visualizing the anal sphincter as a clock face and slowly infiltrating one aliquot to each of the even numbers to produce a field block.

Local Analgesia via Infiltration in Pediatric Patients

The recommended dose of EXPAREL for one-time infiltration in pediatric patients, aged 6 to less than 17 years, is 4 mg/kg (up to a maximum of 266 mg), and is based upon two studies of pediatric patients undergoing either spine surgery or cardiac surgery [see Use in Specific Populations (8.4)].

2.3 Recommended Dose for Regional Analgesia

The maximum recommended dose of EXPAREL via perineural use for interscalene brachial plexus nerve block, sciatic nerve block in the popliteal fossa, and adductor canal block is 133 mg. For all these nerve blocks, administer additional analgesics, which may include other immediate-release local anesthetics, as appropriate (for example, Mayo field block for bunionectomy, infiltration between the popliteal artery and capsule of the knee (IPACK) block for total knee arthroplasty).

Regional Analgesia via Interscalene Brachial Plexus Nerve Block in Adults

The recommended dose of EXPAREL for interscalene brachial plexus nerve block in adults is 133 mg and is based upon one study of patients undergoing either total shoulder arthroplasty or rotator cuff repair [see Clinical Studies (14.3)].

Regional Analgesia via Sciatic Nerve Block in the Popliteal Fossa in Adults

The recommended dose of EXPAREL for sciatic nerve block in the popliteal fossa in adults is 133 mg and is based upon one study of patients undergoing bunionectomy [see Clinical Studies (14.3)].

Regional Analgesia via Adductor Canal Block in Adults

The recommended dose of EXPAREL for adductor canal block in adults is 133 mg (10 mL) admixed with 50 mg (10 mL) 0.5% bupivacaine HCl, for a total volume of 20 mL, and is based upon one study of patients undergoing total knee arthroplasty [see Clinical Studies (14.3)].

2.4 Preparation and Administration Instructions

- Invert vials of EXPAREL multiple times to re-suspend the particles immediately prior to withdrawal from the vial.
- Administer EXPAREL (1) undiluted or (2) diluted to increase volume up to a final concentration of 0.89 mg/mL (i.e., 1:14 dilution by volume) with 0.9% preservative-free Sodium Chloride Injection or lactated Ringer's solution. Use diluted EXPAREL within 4 hours of preparation in a syringe.
- Administer EXPAREL with a 25 gauge or larger bore needle to maintain the structural integrity of the liposomal bupivacaine particles.
- Administer EXPAREL slowly via infiltration or perineural use with frequent aspiration to check for blood and minimize the risk of inadvertent intravascular injection.
- Discard unused portion.

2.5 Compatibility Considerations

Some physicochemical incompatibilities exist between EXPAREL and certain other drugs. Direct contact of EXPAREL with these drugs results in a rapid increase in free (unencapsulated) bupivacaine, altering EXPAREL characteristics and potentially affecting the safety and efficacy of EXPAREL. Therefore, admixing EXPAREL with other drugs prior to administration is not recommended [see Drug Interactions (7)].

- Non-bupivacaine based local anesthetics, including lidocaine, may cause an immediate release of bupivacaine from EXPAREL if administered together locally. The administration of EXPAREL may follow the administration of lidocaine after a delay of 20 minutes or more.
- Bupivacaine HCl administered together with EXPAREL may impact the pharmacokinetic and/or physicochemical properties of EXPAREL, and this effect is concentration dependent. Therefore, bupivacaine HCl and EXPAREL may be administered simultaneously in the same syringe, and bupivacaine HCl may be injected immediately before EXPAREL if the ratio of the milligram dose of bupivacaine HCl solution to EXPAREL does not exceed 1:2.
  The toxic effects of these drugs are additive, and their administration should be used with caution including monitoring for neurologic and cardiovascular effects related to local anesthetic systemic toxicity [see Warnings and Precautions (5.1) and Overdosage (10)].
- When a topical antiseptic such as povidone iodine (e.g., Betadine) is applied, the site should be allowed to dry before EXPAREL is administered into the site. EXPAREL should not be allowed to come into contact with antiseptics such as povidone iodine in solution.

Studies conducted with EXPAREL demonstrated that the most common implantable materials (polypropylene, PTFE, silicone, stainless steel, and titanium) are not affected by the presence of EXPAREL any more than they are by saline. None of the materials studied had an adverse effect on EXPAREL.

3 DOSAGE FORMS AND STRENGTHS

EXPAREL (bupivacaine liposome injectable suspension) is a white to off-white, milky aqueous suspension that is available in the following vial sizes:

- 1.3% (266 mg/20 mL) (13.3 mg/mL) single-dose vial
- 1.3% (133 mg/10 mL) (13.3 mg/mL) single-dose vial

4 CONTRAINDICATIONS

EXPAREL is contraindicated in obstetrical paracervical block anesthesia [see Use in Specific Populations (8.1)]. While EXPAREL has not been tested with this technique, the use of bupivacaine HCl with this technique has resulted in fetal bradycardia and death.

5 WARNINGS AND PRECAUTIONS

5.1 Warnings and Precautions for Bupivacaine-Containing Products

The safety and effectiveness of EXPAREL, other bupivacaine products, and other amide-containing products depend on proper dosage, correct technique, adequate precautions, and readiness for emergencies. As there is a potential risk of severe life-threatening adverse reactions associated with the administration of bupivacaine, any bupivacaine-containing product should be administered in a setting where trained personnel and equipment are available to promptly treat patients who show evidence of neurological or cardiac toxicity [see Overdosage (10)].

Careful and constant monitoring of cardiovascular and respiratory (adequacy of ventilation) vital signs and the patient's state of consciousness should be performed after injection of bupivacaine and other amide-containing products. Restlessness, anxiety, incoherent speech, lightheadedness, numbness and tingling of the mouth and lips, metallic taste, tinnitus, dizziness, blurred vision, tremors, twitching, depression, or drowsiness may be early warning signs of central nervous system toxicity.

EXPAREL, other bupivacaine products, and other amide-containing products should also be used with caution in patients with impaired cardiovascular function because they may be less able to compensate for functional changes associated with the prolongation of AV conduction produced by these drugs.

Injection of multiple doses of EXPAREL, other bupivacaine products, and other amide-containing products may cause significant increases in plasma concentrations with each repeated dose due to slow accumulation of the drug or its metabolites, or to slow metabolic degradation. Tolerance to elevated blood concentrations varies with the status of the patient.

Because amide-type local anesthetics, such as bupivacaine, are metabolized by the liver, these drugs should be used cautiously in patients with hepatic disease. Patients with severe hepatic disease, because of their inability to metabolize local anesthetics normally, are at a greater risk of developing toxic plasma concentrations.

Central Nervous System Reactions

The incidences of adverse neurologic reactions associated with the use of local anesthetics may be related to the total dose of local anesthetic administered and are also dependent upon the particular drug used, the route of administration, and the physical status of the patient. Many of these effects may be related to local anesthetic techniques, with or without a contribution from the drug. Neurologic effects following infiltration of soft tissue may include persistent anesthesia, paresthesia, weakness, and paralysis, all of which may have slow, incomplete, or no recovery.

Central nervous system reactions are characterized by excitation and/or depression. Restlessness, anxiety, dizziness, tinnitus, blurred vision, or tremors may occur, possibly proceeding to convulsions. However, excitement may be transient or absent, with depression being the first manifestation of an adverse reaction. This may quickly be followed by drowsiness merging into unconsciousness and respiratory arrest. Other central nervous system effects may be nausea, vomiting, chills, and constriction of the pupils. The incidence of convulsions associated with the use of local anesthetics varies with the procedure used and the total dose administered.

Cardiovascular System Reactions

Toxic blood concentrations depress cardiac conductivity and excitability, which may lead to atrioventricular block, ventricular arrhythmias, and cardiac arrest, sometimes resulting in fatalities. In addition, myocardial contractility is depressed and peripheral vasodilation occurs, leading to decreased cardiac output and arterial blood pressure [See Overdosage (10)].

Allergic Reactions

Allergic-type reactions are rare and may occur as a result of hypersensitivity to the local anesthetic or to other formulation ingredients. These reactions are characterized by signs such as urticaria, pruritus, erythema, angioneurotic edema (including laryngeal edema), tachycardia, sneezing, nausea, vomiting, dizziness, syncope, excessive sweating, elevated temperature, and possibly anaphylactoid-like symptoms (including severe hypotension). Cross-sensitivity among members of the amide-type local anesthetic group has been reported. The usefulness of screening for sensitivity has not been definitively established.

Chondrolysis

Intra-articular infusions of local anesthetics following arthroscopic and other surgical procedures is an unapproved use, and there have been postmarketing reports of chondrolysis in patients receiving such infusions. The majority of reported cases of chondrolysis have involved the shoulder joint; cases of gleno-humeral chondrolysis have been described in pediatric patients and adult patients following intra-articular infusions of local anesthetics with and without epinephrine for periods of 48 to 72 hours. There is insufficient information to determine whether shorter infusion periods are not associated with these findings. The time of onset of symptoms, such as joint pain, stiffness, and loss of motion can be variable, but may begin as early as the second month after surgery. Currently, there is no effective treatment for chondrolysis; patients who have experienced chondrolysis have required additional diagnostic and therapeutic procedures and some required arthroplasty or shoulder replacement.

Methemoglobinemia

Cases of methemoglobinemia have been reported in association with local anesthetic use. Although all patients are at risk for methemoglobinemia, patients with glucose-6-phosphate dehydrogenase deficiency, congenital or idiopathic methemoglobinemia, cardiac or pulmonary compromise, infants under 6 months of age, and concurrent exposure to oxidizing agents or their metabolites are more susceptible to developing clinical manifestations of the condition. If local anesthetics must be used in these patients, close monitoring for symptoms and signs of methemoglobinemia is recommended.

Signs of methemoglobinemia may occur immediately or may be delayed some hours after exposure, and are characterized by a cyanotic skin discoloration and/or abnormal coloration of the blood. Methemoglobin levels may continue to rise; therefore, immediate treatment is required to avert more serious central nervous system and cardiovascular adverse effects, including seizures, coma, arrhythmias, and death. Discontinue EXPAREL and any oxidizing agents. Depending on the severity of the signs and symptoms, patients may respond to supportive care, i.e., oxygen therapy, hydration. A more severe clinical presentation may require treatment with methylene blue, exchange transfusion, or hyperbaric oxygen.

5.2 Warnings and Precautions Specific for EXPAREL

As there is a potential risk of severe life-threatening adverse reactions associated with the administration of bupivacaine, EXPAREL should be administered in a setting where trained personnel and equipment are available to promptly treat patients who show evidence of neurological or cardiac toxicity [See Overdosage (10)].

Caution should be taken to avoid accidental intravascular injection of EXPAREL. Convulsions and cardiac arrest have occurred following accidental intravascular injection of bupivacaine and other amide-containing products.

Avoid additional use of local anesthetics within 96 hours following administration of EXPAREL [see Dosage and Administration (2.4) and Clinical Pharmacology (12.3)].

EXPAREL has not been evaluated for the following uses and, therefore, is not recommended for these routes of administration or types of analgesia:

- epidural
- intrathecal
- intravascular or intra-articular use
- regional nerve blocks other than interscalene brachial plexus nerve block, sciatic nerve block in the popliteal fossa, and adductor canal block

EXPAREL has not been evaluated for use in the following patient populations and, therefore, is not recommended for administration to these groups.

- patients younger than 6 years old for infiltration
- patients younger than 18 years old for interscalene brachial plexus nerve block, sciatic nerve block in the popliteal fossa, and adductor canal block
- pregnant patients

The potential sensory and/or motor loss with EXPAREL is temporary and varies in degree and duration depending on the site of injection and dose administered and may last for up to 5 days as seen in clinical trials.

6 ADVERSE REACTIONS

The following serious adverse reactions have been associated with bupivacaine hydrochloride in clinical trials and are described in greater detail in other sections of the labeling:

- Central Nervous System Reactions [see Warnings and Precautions (5.1)]
- Cardiovascular System Reactions [see Warnings and Precautions (5.1)]
- Allergic Reactions [see Warnings and Precautions (5.1)]
- Chondrolysis [see Warnings and Precautions (5.1)]
- Methemoglobinemia [see Warnings and Precautions (5.1)]
- Accidental intravascular injection [see Warnings and Precautions (5.2)]

6.1 Clinical Trials Experience

Because clinical studies are conducted under widely varying conditions, adverse reaction rates observed in the clinical trials of a drug cannot be directly compared to rates in the clinical studies of another drug and may not reflect the rates observed in practice.

Adverse Reactions Reported in All Local Infiltration Clinical Studies in Adults

The safety of EXPAREL (local administration into the surgical site) was evaluated in 10 randomized, double-blind, clinical studies (including Studies 1 and 2 [see Clinical Studies (14.2)]) that included 823 adult patients who had various surgical procedures. Patients were administered an EXPAREL dose ranging from 66 to 532 mg (two times the maximum recommended dose of 266 mg). In these studies, following EXPAREL administration, the:

- Most common adverse reactions (incidence greater than or equal to 10%) were nausea, constipation, and vomiting.
- Common adverse reactions (incidence greater than or equal to 2% to less than 10%) were pyrexia, dizziness, peripheral edema, anemia, hypotension, pruritus, tachycardia, headache, insomnia, postoperative anemia, muscle spasms, hemorrhagic anemia, back pain, somnolence, and procedural pain.
- Less common adverse reactions (incidence less than 2%) were chills, erythema, bradycardia, anxiety, urinary retention, pain, edema, tremor, postural dizziness, paresthesia, syncope, incision site edema, procedural hypertension, procedural hypotension, procedural nausea, muscular weakness, neck pain, generalized pruritus, pruritic rash, hyperhidrosis, cold sweat, urticaria, palpitations, sinus bradycardia, supraventricular extrasystoles, ventricular extrasystoles, ventricular tachycardia, hypertension, pallor, anxiety, confusional state, depression, agitation, restlessness, hypoxia, laryngospasm, apnea, respiratory depression, respiratory failure, increased body temperature, increased blood pressure (BP), decreased BP, decreased oxygen saturation, urinary incontinence, blurred vision, tinnitus, drug hypersensitivity, and hypersensitivity.

Neurological and Cardiac Adverse Reactions

In the EXPAREL surgical site infiltration studies, following EXPAREL administration adverse reactions with an incidence greater than or equal to 1% in the:

- Nervous System Disorders system organ class were dizziness (6.2%), headache (3.8%), somnolence (2.1%), hypoesthesia (1.5%), and lethargy (1.3%).
- Cardiac Disorders system organ class were tachycardia (3.9%) and bradycardia (1.6%).

Adverse Reactions Reported in All Local Infiltration Placebo-Controlled Trials in Adults

Adverse reactions with an incidence greater than or equal to 2% reported by adult patients in clinical studies who underwent a bunionectomy (Study 1) or hemorrhoidectomy (Study 2) [see Clinical Studies (14.2)] that compared 106 mg of EXPAREL (8 mL) to placebo and 266 mg of EXPAREL (20 mL) to placebo are shown in Table 1.

Table 1: Treatment-Emergent Adverse Reactions with an Incidence Greater than or Equal to 2%: Local Infiltration Placebo-Controlled Studies in Adults (Studies 1 and 2)
System Organ Class Preferred Term | Study 1 [Study 1: Bunionectomy;] |  | Study 2 [Study 2: Hemorrhoidectomy;]
System Organ Class Preferred Term | EXPAREL | Placebo | EXPAREL | Placebo
System Organ Class Preferred Term | 106 mg (N=97) n (%) | (N=96) n (%) | 266 mg (N=95) n (%) | (N=94) n (%)
Any TEAE | 53 (54.6) | 59 (61.5) | 10 (10.5) | 17 (18.1)
Gastrointestinal Disorders | 41 (42.3) | 38 (39.6) | 7 (7.4) | 13 (13.8)
Nausea | 39 (40.2) | 36 (37.5) | 2 (2.1) | 1 (1.1)
Vomiting | 27 (27.8) | 17 (17.7) | 2 (2.1) | 4 (4.3)
Constipation | 2 (2.1) | 1 (1.0) | 2 (2.1) | 2 (2.1)
Anal Hemorrhage | 0 (0.0) | 0 (0.0) | 3 (3.2) | 4 (4.3)
Painful Defecation | 0 (0.0) | 0 (0.0) | 2 (2.1) | 5 (5.3)
Rectal Discharge | 0 (0.0) | 0 (0.0) | 1 (1.1) | 3 (3.2)
Nervous System Disorders | 20 (20.6) | 30 (31.3) | 0 (0.0) | 0 (0.0)
Dizziness | 11 (11.3) | 25 (26.0) | 0 (0.0) | 0 (0.0)
Headache | 5 (5.2) | 8 (8.3) | 0 (0.0) | 0 (0.0)
Somnolence | 5 (5.2) | 1 (1.0) | 0 (0.0) | 0 (0.0)
Syncope | 2 (2.1) | 0 (0.0) | 0 (0.0) | 0 (0.0)
Skin And Subcutaneous Tissue Disorders | 8 (8.2) | 7 (7.3) | 0 (0.0) | 0 (0.0)
Generalized Pruritus | 5 (5.2) | 6 (6.3) | 0 (0.0) | 0 (0.0)
Pruritus | 3 (3.1) | 1 (1.0) | 0 (0.0) | 0 (0.0)
Investigations | 5 (5.2) | 3 (3.1) | 4 (4.2) | 3 (3.2)
Increased Alanine Aminotransferase | 3 (3.1) | 3 (3.1) | 1 (1.1) | 0 (0.0)
Increased Aspartate Aminotransferase | 3 (3.1) | 2 (2.1) | 0 (0.0) | 0 (0.0)
Increased Blood Creatinine | 2 (2.1) | 0 (0.0) | 0 (0.0) | 0 (0.0)
Increased Body Temperature | 0 (0.0) | 0 (0.0) | 3 (3.2) | 3 (3.2)
General Disorders And Administration Site Conditions | 4 (4.1) | 0 (0.0) | 1 (1.1) | 1 (1.1)
Feeling Hot | 2 (2.1) | 0 (0.0) | 0 (0.0) | 0 (0.0)
Pyrexia | 2 (2.1) | 0 (0.0) | 1 (1.1) | 1 (1.1)
Infections And Infestations | 2 (2.1) | 1 (1.0) | 0 (0.0) | 0 (0.0)
Fungal Infection | 2 (2.1) | 1 (1.0) | 0 (0.0) | 0 (0.0)
Injury, Poisoning And Procedural Complications | 2 (2.1) | 0 (0.0) | 0 (0.0) | 0 (0.0)
Post Procedural Swelling | 2 (2.1) | 0 (0.0) | 0 (0.0) | 0 (0.0)
Metabolism And Nutrition Disorders | 2 (2.1) | 2 (2.1) | 0 (0.0) | 0 (0.0)
Decreased Appetite | 2 (2.1) | 2 (2.1) | 0 (0.0) | 0 (0.0)
TEAE = treatment-emergent adverse event.
At each level of summation (overall, system organ class, preferred term), patients are only counted once. Preferred terms are included where at least 2% of patients reported the event in any treatment group.

Adverse Reactions Reported in All Local Infiltration Clinical Studies in Pediatric Patients Aged 6 to Less Than 17 Years

The safety of EXPAREL in 110 pediatric patients between the age of 6 and 17 years old who had spine or cardiac surgical procedures was evaluated in one randomized, open-label, clinical study in which EXPAREL was administered by infiltration into the surgical site (Study Peds-1) and one single-arm, open-label study in which EXPAREL was administered by infiltration into the surgical site (Study Peds-2) [see Use in Specific Populations (8.4)]. Patients were administered a weight-based dose of EXPAREL at 4 mg/kg (maximum dose of 266 mg) or bupivacaine HCl 2 mg/kg (maximum dose of 175 mg).

In these studies, following EXPAREL administration the:

- Most common adverse reactions (incidence greater than or equal to 10%) were nausea, vomiting, constipation, hypotension, anemia, muscle twitching, blurred vision, pruritus, and tachycardia.
- Common adverse reactions (incidence greater than or equal to 2% to less than 10%) were bradycardia, muscle spasms, tachypnea, oral hypoesthesia, postoperative anemia, dizziness, pyrexia, diarrhea, hypoacusis, hypoesthesia, back pain, hematuria, incontinence, muscular weakness, and visual impairment.
- Less common adverse reactions (incidence less than 2%) were flatulence, abdominal pain, dyspepsia, lip swelling, pain in extremity, musculoskeletal pain, flank pain, musculoskeletal chest pain, hypertension, sinus tachycardia, ventricular extrasystoles, dysgeusia, paresthesia, burning sensation, syncope, diplopia, eye swelling, dyspnea, atelectasis, hypopnea, hypoxia, chest pain, face edema, gait disturbance, generalized pruritus, rash, delayed recovery from anesthesia, fall, incision site hemorrhage, joint dislocation, seroma, hypomagnesemia, acidosis, hyperglycemia, metabolic acidosis, ear discomfort, decreased urine output, increased heart rate (HR), anxiety, panic attack, ear infection, and fungal wound infection.

Neurological and Cardiac Adverse Reactions in Pediatric Patients Aged 6 to Less than 17 Years Old

In the EXPAREL infiltration studies in pediatric patients aged 6 to less than 17 years old (Studies Peds-1 and Peds-2), following EXPAREL administration adverse reactions with an incidence greater than or equal to 1% in the:

- Nervous System Disorders system organ class were dizziness (6.3%, n=5), and dysgeusia (1.3%, n=1).
- Cardiac Disorders system organ class were tachycardia (11.3%, n=9), bradycardia (8.8%, n=7), sinus tachycardia (1.3%, n=1), and ventricular extrasystoles (1.3%, n=1).

Adverse Reactions Reported in All Local Infiltration Trials in Pediatric Patients Aged 6 to Less than 17 Years Old

Adverse reactions with an incidence greater than or equal to 2% reported by patients in clinical studies (Studies Peds-1 and Peds-2) studying 4 mg/kg EXPAREL are shown in Table 2.

Table 2: Treatment-Emergent Adverse Reactions (TEAE) with an Incidence Greater than or Equal to 2%: Local Infiltration Studies in Pediatric Patients Aged 6 to Less than 17 Years Old (Study Peds-1 and Peds-2)
System Organ Class Preferred Term | Study Peds-1 [Study 1: Includes spine surgery patients aged 6 to less than 17 years old, and cardiac surgery patients aged 6 to less than 12 years old.] |  | Study Peds-2 [Study 2: Includes spine surgery patients aged 12 to less than 17 years old.]
System Organ Class Preferred Term | Spine Surgery EXPAREL 4 mg/kg [Patients received EXPAREL 4 mg/kg, not to exceed 266 mg.] (N=36) n (%) | Cardiac Surgery EXPAREL 4 mg/kg (N=29) n (%) | Spine Surgery EXPAREL 4 mg/kg (N=15) n (%)
Patients with at least one TEAE | 24 (66.7) | 9 (31.0) | 15 (100.0)
Blood and lymphatic system disorders | 0 | 0 | 15 (100)
Anemia | 0 | 0 | 15 (100)
Cardiac disorders | 3 (8.3) | 1 (3.4) | 12 (80.0)
Bradycardia | 2 (5.6) | 0 | 5 (33.3)
Sinus tachycardia | 0 | 1 (3.4) | 0
Tachycardia | 1 (2.8) | 0 | 8 (53.3)
Ventricular extrasystoles | 0 | 0 | 1 (6.7)
Ear and labyrinth disorders | 2 (5.6) | 0 | 2 (13.3)
Ear discomfort | 0 | 0 | 1 (6.7)
Hypoacusis | 2 (5.6) | 0 | 1 (6.7)
Eye disorders | 10 (27.8) | 1 (3.4) | 4 (26.7)
Diplopia | 1 (2.8) | 0 | 0
Eye swelling | 0 | 0 | 1 (6.7)
Increased Lacrimation | 0 | 0 | 0
Blurred Vision | 7 (19.4) | 1 (3.4) | 3 (20.0)
Visual impairment | 2 (5.6) | 0 | 0
Gastrointestinal disorders | 18 (50.0) | 7 (24.1) | 14 (93.3)
Abdominal Pain | 0 | 0 | 1 (6.7)
Constipation | 9 (25.0) | 4 (13.8) | 7 (46.7)
Nausea | 11 (30.6) | 2 (6.9) | 9 (60.0)
Diarrhea | 3 (8.3) | 0 | 0
Dyspepsia | 1 (2.8) | 0 | 0
Flatulence | 0 | 0 | 1 (6.7)
Oral Hypoesthesia | 4 (11.1) | 0 | 2 (13.3)
Lip Swelling | 0 | 0 | 1 (6.7)
Vomiting | 10 (27.8) | 4 (13.8) | 8 (53.3)
General disorders and administration site conditions | 0 | 1 (3.4) | 3 (20.0)
Chest pain | 1 (2.8) | 0 | 0
Face edema | 0 | 1 (3.4) | 0
Gait disturbance | 0 | 0 | 1 (6.7)
Generalized edema | 0 | 0 | 0
Pyrexia | 0 | 0 | 3 (20.0)
Infections and infestations | 1 (2.8) | 1 (3.4) | 0
Ear infection | 1 (2.8) | 0 | 0
Fungal wound infection | 0 | 1 (3.4) | 0
Injury, poisoning and procedural complications | 8 (22.2) | 0 | 1 (6.7)
Postoperative Anemia | 5 (13.9) | 0 | 0
Delayed recovery from anesthesia | 1 (2.8) | 0 | 0
Fall | 0 | 0 | 1 (6.7)
Incision site hemorrhage | 1 (2.8) | 0 | 0
Joint dislocation | 1 (2.8) | 0 | 0
Procedural hemorrhage | 0 | 0 | 0
Seroma | 1 (2.8) | 0 | 0
Metabolism and nutrition disorders | 0 | 3 (10.3) | 0
Acidosis | 0 | 1 (3.4) | 0
Hyperglycemia | 0 | 1 (3.4) | 0
Hypomagnesaemia | 0 | 1 (3.4) | 0
Metabolic acidosis | 0 | 1 (3.4) | 0
Musculoskeletal and connective tissue disorders | 8 (22.2) | 1 (3.4) | 12 (80.0)
Back pain | 0 | 0 | 2 (13.3)
Flank pain | 0 | 0 | 1 (6.7)
Muscle twitching | 3 (8.3) | 1 (3.4) | 9 (60.0)
Muscle spasms | 4 (11.1) | 0 | 3 (20.0)
Muscular weakness | 0 | 0 | 2 (13.3)
Musculoskeletal pain | 1 (2.8) | 0 | 0
Musculoskeletal chest pain | 0 | 0 | 1 (6.7)
Pain in extremity | 0 | 0 | 1 (6.7)
Nervous system disorders | 3 (8.3) | 0 | 7 (46.7)
Burning sensation | 0 | 0 | 1 (6.7)
Dizziness | 2 (5.6) | 0 | 3 (20.0)
Dysgeusia | 1 (2.8) | 0 | 0
Headache | 0 | 0 | 0
Hypoesthesia | 0 | 0 | 3 (20.0)
Paresthesia | 0 | 0 | 1 (6.7)
Syncope | 1 (2.8) | 0 | 0
Psychiatric disorders |  | 0 | 2 (13.3)
Anxiety | 0 | 0 | 1 (6.7)
Panic attack | 0 | 0 | 1 (6.7)
Renal and urinary disorders | 0 | 0 | 2 (13.3)
Hematuria | 0 | 0 | 2 (13.3)
Respiratory, thoracic and mediastinal disorders | 3 (8.3) | 1 (3.4) | 7 (46.7)
Atelectasis | 0 | 0 | 1 (6.7)
Bradypnea | 0 | 0 | 0
Dyspnea | 0 | 1 (3.4) | 0
Hypopnea | 1 (2.8) | 0 | 0
Hypoxia | 1 (2.8) | 0 | 0
Pleural effusion | 0 | 0 | 0
Tachypnea | 1 (2.8) | 0 | 6 (40.0)
Skin and subcutaneous tissue disorders | 4 (11.1) | 0 | 6 (40.0)
Pruritus | 3 (8.3) | 0 | 6 (40.0)
Generalized Pruritus | 1 (2.8) | 0 | 0
Rash | 0 | 0 | 1 (6.7)
Vascular disorders | 4 (11.1) | 1 (3.4) | 14 (93.3)
Hot flush | 0 | 0 | 0
Hypotension | 4 (11.1) | 0 | 14 (93.3)
Hypertension | 0 | 1 (3.4) | 0
Systolic hypertension | 0 | 0 | 0
At each level of summation (overall, system organ class, preferred term), patients are only counted once. Preferred terms are included where at least 2% of patients reported the event in any treatment group.
TEAE = treatment-emergent adverse event.

Adverse Reactions Reported in Placebo-Controlled Nerve Block Clinical Studies in Adults

The safety of EXPAREL was evaluated in four randomized, double-blind, placebo-controlled nerve block clinical studies (Studies 3, 6, 7, 8) [see Clinical Studies (14.3, 14.4)] involving 469 EXPAREL-treated adult patients and 357 placebo-treated patients who had various surgical procedures. Patients were administered placebo or an EXPAREL dose of either 133 or 266 mg (two times the maximum recommended dose for these nerve blocks). In these studies, following EXPAREL administration via nerve block (perineural use) the:

- Most common adverse reactions (incidence greater than or equal to 10%) were nausea, pyrexia, and constipation.
- Common adverse reactions (incidence greater than or equal to 2% to less than 10%) were muscle twitching, dysgeusia, urinary retention, fatigue, headache, confusional state, hypotension, hypertension, oral hypoesthesia, generalized pruritus, hyperhidrosis, tachycardia, sinus tachycardia, anxiety, fall, increased body temperature, peripheral edema, sensory loss, increased hepatic enzyme, hiccups, hypoxia, and post-procedural hematoma.
- Less common adverse reactions (incidence less than 2%) were arrhythmia, atrial fibrillation, first degree atrioventricular block, bradycardia, left bundle branch block, right bundle branch block, cardiac arrest, impaired hearing, blurred vision, visual impairment, asthenia, chills, hyperthermia, cellulitis, lung infection, pneumonia, procedural nausea, wound dehiscence, wound secretion, electrocardiogram QT prolonged, white blood cell count increased, arthralgia, back pain, joint swelling, decreased mobility, muscle spasms, muscular weakness, musculoskeletal pain, paraesthesia, presyncope, sedation, somnolence, syncope, delirium, dysuria, urinary incontinence, atelectasis, cough, dyspnea, lung infiltration, blister, drug eruption, erythema, rash, urticaria, deep vein thrombosis, hematoma, and orthostatic hypotension.

The most common and common adverse reactions for the four randomized, double-blind, placebo-controlled nerve block clinical studies (Studies 3, 6, 7, 8) are shown in Table 3.

Neurological and Cardiac Adverse Reactions

In the EXPAREL nerve block placebo-controlled studies, following EXPAREL administration adverse reactions with an incidence greater than or equal to 1% in the:

- Nervous System Disorders system organ class were motor dysfunction (14.9%), dysgeusia (7.2%), headache (5.1%), hypoesthesia (2.3%), and sensory loss (2.3%).
- Cardiac Disorders system organ class were tachycardia (3%), sinus tachycardia (2.3%), and bradycardia (1.3%).

Table 3: Treatment-Emergent Adverse Reactions with an Incidence Greater than or Equal to 2%: Nerve Block Placebo-Controlled Studies (Studies 3, 6, 7, and 8)
SYSTEM ORGAN CLASS Preferred Term | EXPAREL 133 mg (N=168) n (%) | EXPAREL 266 mg (N=301) n (%) | Placebo (N=357) n (%)
Number of Patients with at Least One TEAE | 152 (90.5) | 260 (86.4) | 299 (83.8)
Blood and Lymphatic System Disorders | 2 (1.2) | 22 (7.3) | 15 (4.2)
Anemia | 2 (1.2) | 18 (6.0) | 13 (3.6)
Cardiac Disorders | 13 (7.7) | 34 (11.3) | 38 (10.6)
Atrial Fibrillation | 1 (0.6) | 4 (1.3) | 8 (2.2)
Sinus Tachycardia | 3 (1.8) | 8 (2.7) | 4 (1.1)
Tachycardia | 3 (1.8) | 11 (3.7) | 10 (2.8)
Gastrointestinal Disorders | 84 (50.0) | 154 (51.2) | 184 (51.5)
Constipation | 29 (17.3) | 66 (21.9) | 68 (19.0)
Dyspepsia | 3 (1.8) | 7 (2.3) | 7 (2.0)
Oral Hypoesthesia | 6 (3.6) | 8 (2.7) | 7 (2.0)
Nausea | 62 (36.9) | 111 (36.9) | 133 (37.3)
Vomiting | 17 (10.1) | 55 (18.3) | 73 (20.4)
General Disorders And Administration Site Conditions | 52 (31.0) | 102 (33.9) | 91 (25.5)
Fatigue | 7 (4.2) | 15 (5.0) | 15 (4.2)
Feeling Cold | 0 | 10 (3.3) | 8 (2.2)
Peripheral Edema | 4 (2.4) | 6 (2.0) | 8 (2.2)
Peripheral Swelling | 3 (1.8) | 8 (2.7) | 4 (1.1)
Pyrexia | 36 (21.4) | 70 (23.3) | 64 (17.9)
Injury, Poisoning And Procedural Complications | 18 (10.7) | 44 (14.6) | 32 (9.0)
Postoperative Anemia | 0 | 8 (2.7) | 10 (2.8)
Contusion | 4 (2.4) | 1 (0.3) | 0
Fall | 4 (2.4) | 8 (2.7) | 1 (0.3)
Post Procedural Hematoma | 4 (2.4) | 1 (0.3) | 0
Procedural Hypotension | 2 (1.2) | 13 (4.3) | 7 (2.0)
Investigations | 18 (10.7) | 31 (10.3) | 31 (8.7)
Increased Body Temperature | 1 (0.6) | 10 (3.3) | 4 (1.1)
Increased Hepatic Enzyme | 7 (4.2) | 1 (0.3) | 3 (0.8)
Metabolism and Nutrition Disorders | 13 (7.7) | 18 (6.0) | 25 (7.0)
Hypokalemia | 7 (4.2) | 9 (3.0) | 14 (3.9)
Musculoskeletal And Connective Tissue Disorders | 22 (13.1) | 47 (15.6) | 41 (11.5)
Decreased Mobility | 0 | 6 (2.0) | 5 (1.4)
Muscle Twitching | 14 (8.3) | 21 (7.0) | 25 (7.0)
Nervous System Disorders | 72 (42.9) | 101 (33.6) | 112 (31.4)
Dizziness | 8 (4.8) | 28 (9.3) | 40 (11.2)
Dysgeusia | 12 (7.1) | 22 (7.3) | 21 (5.9)
Headache | 14 (8.3) | 10 (3.3) | 10 (2.8)
Hypoesthesia | 6 (3.6) | 5 (1.7) | 2 (0.6)
Motor Dysfunction | 35 (20.8) | 35 (11.6) | 37 (10.4)
Sensory Loss | 4 (2.4) | 7 (2.3) | 1 (0.3)
Psychiatric Disorders | 10 (6.0) | 33 (11.0) | 44 (12.3)
Anxiety | 3 (1.8) | 9 (3.0) | 6 (1.7)
Confusional State | 3 (1.8) | 15 (5.0) | 14 (3.9)
Insomnia | 5 (3.0) | 10 (3.3) | 19 (5.3)
Renal And Urinary Disorders | 9 (5.4) | 31 (10.3) | 31 (8.7)
Urinary Retention | 5 (3.0) | 23 (7.6) | 22 (6.2)
Respiratory, Thoracic And Mediastinal Disorders | 18 (10.7) | 30 (10.0) | 31 (8.7)
Dyspnea | 2 (1.2) | 4 (1.3) | 8 (2.2)
Hiccups | 4 (2.4) | 4 (1.3) | 1 (0.3)
Hypoxia | 4 (2.4) | 3 (1.0) | 3 (0.8)
Skin And Subcutaneous Tissue Disorders | 24 (14.3) | 63 (20.9) | 84 (23.5)
Hyperhidrosis | 1 (0.6) | 14 (4.7) | 15 (4.2)
Pruritus | 10 (6.0) | 45 (15.0) | 55 (15.4)
Generalized Pruritus | 6 (3.6) | 7 (2.3) | 14 (3.9)
Vascular Disorders | 16 (9.5) | 30 (10.0) | 44 (12.3)
Hypertension | 3 (1.8) | 15 (5.0) | 21 (5.9)
Hypotension | 11 (6.5) | 8 (2.7) | 19 (5.3)
At each level of summation (overall, system organ class, preferred term), patients are only counted once.
Preferred terms are included where at least 2% of patients reported the event in any treatment group.
TEAE = treatment-emergent adverse event.

Adverse Reactions Reported in Active-Controlled Nerve Block Clinical Studies in Approved Populations

The safety of EXPAREL was evaluated in two randomized, double-blind, active-controlled nerve block clinical studies in 189 adult patients who had a bunionectomy or a total knee arthroplasty (Studies 4 and 5) [see Clinical Studies (14.3)]. Via nerve block, patients received 133 mg of EXPAREL, 266 mg of EXPAREL (two times the maximum recommended EXPAREL dose) [see Dosage and Administration (2.3)] or 133 mg of EXPAREL admixed with 50 mg of bupivacaine HCl. In both of these studies the active comparator was 50 mg of bupivacaine HCl.

The most common adverse reactions (incidence greater than or equal to 10%) in Studies 4 and 5 following:

- EXPAREL administration as a nerve block were nausea and constipation.
- Administration of EXPAREL admixed with bupivacaine as a nerve block were nausea, constipation, muscle spasms, and headache.

The common adverse reactions (incidence greater than or equal to 2% to less than 10%) in Studies 4 and 5 following:

- EXPAREL administration as a nerve block were pruritus, vomiting, dyspepsia, headache, peroneal nerve palsy, rash and hypertension.
- Administration of EXPAREL admixed with bupivacaine as a nerve block were vomiting, dyspepsia, heart rate increased, hypokalaemia, hyponatraemia, back pain, disorientation, oropharyngeal pain, hypoaesthesia, pruritus, dizziness, insomnia, hypertension, hypoxia, hypotension, pyrexia, and tachycardia.

The less common adverse reactions (incidence less than 2%) in Studies 4 and 5 following:

- EXPAREL administration as a nerve block were increased BP, pyrexia, arthralgia, insomnia, muscle spasms, asthenia, increased systolic BP, diarrhea, facial pain, migraine, muscle twitching, throat irritation, post procedural erythema, post procedural edema, dizziness, hypoesthesia, rhinorrhea, and paresthesia.
- Administration of EXPAREL admixed with bupivacaine as a nerve block were increased BP, procedural pain, rash, pruritic rash, anemia, anxiety, arthralgia, atrial fibrillation, decreased blood potassium, decreased BP, increased systolic BP, increased body temperature, bradycardia, confusional state, decreased appetite, diarrhea, dysarthria, fall, feeling cold, decreased HR, hot flush, joint swelling, leukocytosis, mental status changes, neuralgia, orthostatic hypotension, decreased oxygen saturation, pneumonia, post procedural hematoma, post procedural inflammation, post procedural swelling, pruritic rash, positive staphylococcus test, syncope, and urinary tract infection .

The most common and common adverse reactions in adult patients in the active-controlled clinical studies are shown in Table 4.

Table 4: Treatment-Emergent Adverse Reactions with an Incidence Greater than or Equal to 2%: Nerve Block Active-Controlled Studies (Studies 4 and 5)
SYSTEM ORGAN CLASS Preferred Term | EXPAREL 133 mg (N=81) n (%) | EXPAREL 266 mg (N=22) n (%) | EXPAREL 133 mg + Bupi (N = 86) n (%) | Bupi (N=162) n (%)
Number of Patients with at Least One TEAE | 42 (51.9) | 13 (59.1) | 77 (89.5) | 116 (71.6)
Cardiac Disorders
Tachycardia | 0 | 0 | 4 (4.7) | 5 (3.1)
Gastrointestinal Disorders
Constipation | 10 (12.3) | 3 (13.6) | 30 (34.9) | 47 (29.0)
Dyspepsia | 2 (2.5) | 1 (4.5) | 2 (2.3) | 2 (1.2)
Nausea | 13 (16) | 9 (40.9) | 34 (39.5) | 49 (30.2)
Vomiting | 4 (4.9) | 5 (22.7) | 5 (5.8) | 13 (8.0)
General Disorders And Administration Site Conditions
Pyrexia | 0 | 1 (4.5) | 3 (3.5) | 3 (1.9)
Investigations
Increased Heart rate | 0 | 0 | 3 (3.5) | 3 (1.9)
Metabolism and Nutrition Disorders
Hypokalemia | 0 | 0 | 2 (2.3) | 2 (1.2)
Hyponatremia | 0 | 0 | 2 (2.3) | 2 (1.2)
Musculoskeletal And Connective Tissue Disorders
Back pain | 0 | 0 | 2 (2.3) | 3 (1.9)
Muscle Spasms | 2 (2.5) | 0 | 11 (12.8) | 10 (6.2)
Nervous System Disorders
Dizziness | 2 (2.5) | 0 | 4 (4.7) | 4 (2.5)
Headache | 8 (9.9) | 1 (4.5) | 13 (15.1) | 6 (3.7)
Hypoaesthesia | 0 | 9 (12.7) | 2 (2.1) | 0
Peroneal Nerve Palsy | 3 (3.7) | 0 | 0 | 0
Psychiatric Disorders
Disorientation | 0 | 0 | 2 (2.3) | 0
Insomnia | 2 (2.5) | 0 | 5 (5.8) | 14 (8.6)
Respiratory, Thoracic And Mediastinal Disorders
Hypoxia | 0 | 0 | 4 (4.7) | 4 (2.5)
Oropharyngeal Pain | 0 | 0 | 2 (2.3) | 0
Skin And Subcutaneous Tissue Disorders
Pruritus | 6 (7.4) | 1 (4.5) | 6 (7.0) | 9 (5.6)
Rash | 4 (4.9) | 1 (4.5) | 1 (1.2) | 1 (0.6)
Vascular Disorders
Hypertension | 3 (3.7) | 1 (4.5) | 5 (5.8) | 7 (4.3)
Hypotension | 0 | 0 | 3 (3.5) | 9 (5.6)
At each level of summation (overall, system organ class, preferred term), patients were only counted once.
Preferred terms are included where at least 2% of patients reported the event in any treatment group.
TEAE = treatment-emergent adverse event.

Notable Adverse Reactions from Active-Controlled Studies in Unapproved Populations

The safety of EXPAREL was evaluated in a multicenter, randomized, double-blind, active-controlled trial in 119 patients undergoing foot and ankle procedures (Study 9) [see Clinical Studies (14.3)]. Patients were administered a dose of either 266 mg EXPAREL, 266 mg EXPAREL admixed with 50 mg bupivacaine HCl, or 100 mg bupivacaine HCl. The following adverse reactions were observed following administration of EXPAREL or EXPAREL admixed with bupivacaine in Study 9 that either were not observed in Studies 4 and 5, or were observed at a higher frequency than was observed in Studies 4 and 5. These include:

- The most common adverse reactions (incidence greater than 10%) observed in Study 9 at higher frequencies than Studies 4 and 5: hypoesthesia (21% vs. 1% and 0%, respectively), paresthesia (10% vs. 1% and 0%, respectively).
- The common adverse reactions (incidence greater than or equal to 2% to less than 10%) observed in Study 9 but not in Studies 4 and 5: epistaxis, motor dysfunction, pain in extremity, skin abrasion, infusion site pain, muscular weakness.

6.2 Postmarketing Experience

Because adverse reactions reported during postmarketing are reported voluntarily from a population of uncertain size, it is not always possible to reliably estimate their frequency or establish a causal relationship to drug exposure.

These adverse reactions are consistent with those observed in clinical studies and most commonly involve the following system organ classes: Injury, Poisoning, and Procedural Complications (e.g., drug-drug interaction, procedural pain), Nervous System Disorders (e.g., palsy, seizure), General Disorders And Administration Site Conditions (e.g., lack of efficacy, pain), Skin And Subcutaneous Tissue Disorders (e.g., erythema, rash), and Cardiac Disorders (e.g., bradycardia, cardiac arrest).

7 DRUG INTERACTIONS

The toxic effects of local anesthetics are additive and concomitant use should be used with caution including monitoring for neurologic and cardiovascular effects related to local anesthetic systemic toxicity [see Dosage and Administration (2.2), Warnings and Precautions (5.1), and Overdosage (10)]. Avoid additional use of local anesthetics within 96 hours following administration of EXPAREL.

Patients who are administered local anesthetics, including EXPAREL, may be at increased risk of developing methemoglobinemia when concurrently exposed to the following drugs, which could include other local anesthetics:

Class | Examples
Nitrates/Nitrites | nitric oxide, nitroglycerin, nitroprusside, nitrous oxide
Local anesthetics | articaine, benzocaine, bupivacaine, lidocaine, mepivacaine, prilocaine, procaine, ropivacaine, tetracaine
Antineoplastic agents | cyclophosphamide, flutamide, hydroxyurea, ifosfamide, rasburicase
Antibiotics | dapsone, nitrofurantoin, para-aminosalicylic acid, sulfonamides
Antimalarials | chloroquine, primaquine
Anticonvulsants | Phenobarbital, phenytoin, sodium valproate
Other drugs | acetaminophen, metoclopramide, quinine, sulfasalazine

Bupivacaine

Bupivacaine HCl administered together with EXPAREL may impact the pharmacokinetic and/or physicochemical properties of EXPAREL, and this effect is concentration dependent. Therefore, bupivacaine HCl and EXPAREL may be administered simultaneously in the same syringe, and bupivacaine HCl may be injected immediately before EXPAREL as long as the ratio of the milligram dose of bupivacaine HCl solution to EXPAREL does not exceed 1:2.

Non-Bupivacaine Local Anesthetics

EXPAREL should not be admixed with local anesthetics other than bupivacaine. Non-bupivacaine based local anesthetics, including lidocaine, may cause an immediate release of bupivacaine from EXPAREL if administered together locally. The administration of EXPAREL may follow the administration of lidocaine after a delay of 20 minutes or more. There are no data to support administration of other local anesthetics prior to administration of EXPAREL.

Other than bupivacaine as noted above, EXPAREL should not be admixed with other drugs prior to administration.

Water and Hypotonic Agents

Do not dilute EXPAREL with water or other hypotonic agents, as it will result in disruption of the liposomal particles.

8 USE IN SPECIFIC POPULATIONS

8.1 Pregnancy

Risk Summary

There are no studies conducted with EXPAREL in pregnant women. In animal reproduction studies, embryo-fetal deaths were observed with subcutaneous administration of bupivacaine to rabbits during organogenesis at a dose equivalent to 1.6 times the maximum recommended human dose (MRHD) of 266 mg. Subcutaneous administration of bupivacaine to rats from implantation through weaning produced decreased pup survival at a dose equivalent to 1.5 times the MRHD [see Data]. Based on animal data, advise pregnant women of the potential risks to a fetus.

The background risk of major birth defects and miscarriage for the indicated population is unknown. However, the background risk in the U.S. general population of major birth defects is 2-4% and of miscarriage is 15-20% of clinically recognized pregnancies.

Clinical Considerations

Labor or Delivery

Bupivacaine is contraindicated for obstetrical paracervical block anesthesia. While EXPAREL has not been studied with this technique, the use of bupivacaine for obstetrical paracervical block anesthesia has resulted in fetal bradycardia and death.

Bupivacaine can rapidly cross the placenta, and when used for epidural, caudal, or pudendal block anesthesia, can cause varying degrees of maternal, fetal, and neonatal toxicity [See Clinical Pharmacology (12.3)]. The incidence and degree of toxicity depend upon the procedure performed, the type, and amount of drug used, and the technique of drug administration. Adverse reactions in the parturient, fetus, and neonate involve alterations of the central nervous system, peripheral vascular tone, and cardiac function.

Data

Animal Data

Bupivacaine hydrochloride was administered subcutaneously to rats and rabbits during the period of organogenesis (implantation to closure of the hard plate). Rat doses were 4.4, 13.3, and 40 mg/kg/day (equivalent to 0.2, 0.5 and 1.5 times the MRHD, respectively, based on the BSA comparisons and a 60 kg human weight) and rabbit doses were 1.3, 5.8, and 22.2 mg/kg/day (equivalent to 0.1, 0.4 and 1.6 times the MRHD, respectively, based on the BSA comparisons and a 60 kg human weight). No embryo-fetal effects were observed in rats at the doses tested with the high dose causing increased maternal lethality. An increase in embryo-fetal deaths was observed in rabbits at the high dose in the absence of maternal toxicity.

Decreased pup survival was noted at 1.5 times the MRHD in a rat pre- and post-natal development study when pregnant animals were administered subcutaneous doses of 4.4, 13.3, and 40 mg/kg/day bupivacaine hydrochloride (equivalent to 0.2, 0.5 and 1.5 times the MRHD, respectively, based on the BSA comparisons and a 60 kg human weight) from implantation through weaning (during pregnancy and lactation).

8.2 Lactation

Risk Summary

Limited published literature reports that bupivacaine and its metabolite, pipecoloxylidide, are present in human milk at low levels. There is no available information on effects of the drug in the breastfed infant or effects of the drug on milk production. The developmental and health benefits of breastfeeding should be considered along with the mother's clinical need for EXPAREL and any potential adverse effects on the breastfed infant from EXPAREL or from the underlying maternal condition.

8.4 Pediatric Use

The safety and effectiveness of EXPAREL to produce postsurgical local analgesia via infiltration have been established in pediatric patients aged 6 years and older. Use of EXPAREL for this indication is supported by evidence from adequate and well-controlled studies in adults, and pharmacokinetic (PK) and safety data in pediatric patients aged 6 years and older from Studies Peds-1 and Peds-2 [see Adverse Reactions (6.1), Clinical Pharmacology (12.3)].

- Study Peds-1 was a multicenter, randomized, open-label, two-part study (NCT03682302) to evaluate the PK and safety of EXPAREL for local infiltration in pediatric patients aged 6 to less than 17 years who were undergoing spine or cardiac surgery (postsurgically, patients were administered opioid rescue medication according to the study site's standard of care).
  - Group 1: 61 patients aged 12 to less than 17 years, undergoing spine surgeries, were randomized 1:1 to receive either EXPAREL 4 mg/kg (maximum 266 mg) or bupivacaine HCl 2 mg/kg (maximum 175 mg).
  - Group 2: 34 patients aged 6 to less than 12 years, undergoing either spine or cardiac surgeries, received open-label EXPAREL 4 mg/kg (maximum up to 266 mg).
- Study Peds-2 was a phase 1, open-label study that evaluated the PK and safety of 4 mg/kg (maximum 266 mg) of EXPAREL (administered intraoperatively prior to wound closure) in 15 pediatric patients aged 12 to less than 17 who were undergoing spinal surgery.

The safety and effectiveness of EXPAREL have not been established to produce postsurgical:

- Local analgesia via infiltration in pediatric patients aged less than 6 years old.
- Regional analgesia via an interscalene brachial plexus nerve block, sciatic nerve block in the popliteal fossa, or adductor canal block in pediatric patients.

8.5 Geriatric Use

Of the total number of patients in the EXPAREL local infiltration clinical studies (N=823), 171 patients were greater than or equal to 65 years of age and 47 patients were greater than or equal to 75 years of age. Of the total number of patients in the EXPAREL nerve block clinical studies (N= 1046), 312 patients were greater than or equal to 65 years of age and 70 patients were greater than or equal to 75 years of age. No overall differences in safety or effectiveness of EXPAREL have been observed between patients 65 years of age and older and younger adult patients.

In clinical studies, differences in various pharmacokinetic parameters have been observed between patients 65 years of age and older and younger adult patients. Bupivacaine is known to be substantially excreted by the kidney, and the risk of adverse reactions to bupivacaine may be greater in patients with renal impairment than in patients with normal renal function. Because patients 65 years of age and older are more likely to have renal impairment, increase monitoring for EXPAREL-associated adverse reactions [see Adverse Reactions (6)].

8.6 Hepatic Impairment

Amide-type local anesthetics, such as bupivacaine, are metabolized by the liver. Patients with severe hepatic disease, because of their inability to metabolize local anesthetics normally, are at a greater risk of developing toxic plasma concentrations, and potentially local anesthetic systemic toxicity [see Clinical Pharmacology (12.3)]. Therefore, consider increased monitoring for local anesthetic systemic toxicity in patients with moderate to severe hepatic disease.

8.7 Renal Impairment

Bupivacaine is known to be substantially excreted by the kidney, and the risk of adverse reactions to EXPAREL may be greater in patients with renal impairment than in patients with normal renal function. Therefore, in patients with renal impairment, increase monitoring for EXPAREL-associated adverse reactions [see Adverse Reactions (6)].

10 OVERDOSAGE

Clinical Presentation

Acute emergencies from local anesthetics are generally related to high plasma concentrations encountered during therapeutic use of local anesthetics or to unintended intravascular injection of local anesthetic solution [See Warnings and Precautions (5) and Adverse Reactions (6)].

Signs and symptoms of overdose include CNS symptoms (perioral paresthesia, dizziness, dysarthria, confusion, mental obtundation, sensory and visual disturbances, and eventually convulsions) and cardiovascular effects (that range from hypertension and tachycardia to myocardial depression, hypotension, bradycardia, and asystole).

Plasma levels of bupivacaine associated with toxicity can vary. Although concentrations of 2,500 to 4,000 ng/mL have been reported to elicit early subjective CNS symptoms of bupivacaine toxicity, symptoms of toxicity have been reported at levels as low as 800 ng/mL.

Management of Local Anesthetic Overdose

At the first sign of change, oxygen should be administered.

The first step in the management of convulsions, as well as underventilation or apnea, consists of immediate attention to the maintenance of a patent airway and assisted or controlled ventilation with oxygen and a delivery system capable of permitting immediate positive airway pressure by mask. Immediately after the institution of these ventilatory measures, the adequacy of the circulation should be evaluated, keeping in mind that drugs used to treat convulsions sometimes depress the circulation when administered intravenously. Should convulsions persist despite adequate respiratory support, and if the status of the circulation permits, small increments of an ultra-short acting barbiturate (such as thiopental or thiamylal) or a benzodiazepine (such as diazepam) may be administered intravenously. The clinician should be familiar, prior to the use of anesthetics, with these anticonvulsant drugs. Supportive treatment of circulatory depression may require administration of intravenous fluids and, when appropriate, a vasopressor dictated by the clinical situation (such as ephedrine to enhance myocardial contractile force).

If not treated immediately, both convulsions and cardiovascular depression can result in hypoxia, acidosis, bradycardia, arrhythmias, and cardiac arrest. If cardiac arrest should occur, standard cardiopulmonary resuscitative measures should be instituted.

Endotracheal intubation, employing drugs and techniques familiar to the clinician, may be indicated, after initial administration of oxygen by mask, if difficulty is encountered in the maintenance of a patent airway or if prolonged ventilatory support (assisted or controlled) is indicated.

11 DESCRIPTION

EXPAREL (bupivacaine liposome injectable suspension) is a sterile, non-pyrogenic white to off-white preservative-free aqueous suspension consisting of multivesicular liposomes containing bupivacaine. Bupivacaine is present at a concentration of 13.3 mg/mL. After injection of EXPAREL, bupivacaine is released from the multivesicular liposomes. EXPAREL is for infiltration or perineural use.

Active Ingredient

Bupivacaine is related chemically and pharmacologically to the amide-type local anesthetics. It is a homologue of mepivacaine and is related chemically to lidocaine. All three of these anesthetics contain an amide linkage between the aromatic nucleus and the amino, or piperidine group. They differ in this respect from the procaine-type local anesthetics, which have an ester linkage. Chemically, bupivacaine is 1-butyl-N-(2,6-dimethylphenyl)-2-piperidinecarboxamide with a molecular weight of 288.4. Bupivacaine has the following structural formula:

EXPAREL

The median diameter of the liposome particles in EXPAREL ranges from 24 to 31 μm. The liposomes are suspended in a 0.9% Sodium Chloride Injection. Each vial contains bupivacaine at a nominal concentration of 13.3 mg/mL. Inactive ingredients and their nominal concentrations are: cholesterol, 4.7 mg/mL; 1, 2-dipalmitoyl-sn-glycero-3 phospho-rac-(1-glycerol) sodium salt (DPPG), 0.9 mg/mL; tricaprylin, 2.0 mg/mL; 1, 2-dierucoylphosphatidylcholine (DEPC), 8.2 mg/mL; phosphoric acid to adjust pH; and sodium chloride to adjust tonicity. The pH of EXPAREL is in the range of 5.8 to 7.4.

Bupivacaine in EXPAREL has different functional properties relative to those of the unencapsulated or nonlipid-associated bupivacaine products. Bupivacaine that is released from EXPAREL has a different pharmacokinetic and systemic profile relative to other bupivacaine products. In addition, the nominal weight percent concentration of bupivacaine in EXPAREL is based on bupivacaine free base rather than bupivacaine HCl (100 mg of bupivacaine HCl contains 88.6 mg of bupivacaine free base) [see Dosage and Administration (2.1)].

12 CLINICAL PHARMACOLOGY

12.1 Mechanism of Action

Local anesthetics block the generation and the conduction of nerve impulses presumably by increasing the threshold for electrical excitation in the nerve, by slowing the propagation of the nerve impulse, and by reducing the rate of rise of the action potential. In general, the progression of anesthesia is related to the diameter, myelination, and conduction velocity of affected nerve fibers. Clinically, the order of loss of nerve function is as follows: (1) pain, (2) temperature, (3) touch, (4) proprioception, and (5) skeletal muscle tone.

12.2 Pharmacodynamics

Systemic absorption of local anesthetics produces effects on the cardiovascular and central nervous systems. At blood concentrations achieved with normal therapeutic doses, changes in cardiac conduction, excitability, refractoriness, contractility, and peripheral vascular resistance are minimal. However, toxic blood concentrations depress cardiac conductivity and excitability, which may lead to atrioventricular block, ventricular arrhythmias, and cardiac arrest, sometimes resulting in fatalities. In addition, myocardial contractility is depressed and peripheral vasodilation occurs, leading to decreased cardiac output and arterial blood pressure. Clinical reports and animal research suggest that these cardiovascular changes are more likely to occur after accidental intravascular injection of bupivacaine.

Following systemic absorption, local anesthetics can produce central nervous system stimulation, depression, or both. Apparent central stimulation is manifested as restlessness, tremors, and shivering progressing to convulsions, followed by depression and coma progressing ultimately to respiratory arrest. However, the local anesthetics have a primary depressant effect on the medulla and on higher centers. The depressed stage may occur without a prior excited state.

12.3 Pharmacokinetics

After administration of EXPAREL, the systemic plasma levels of bupivacaine were observed for 96 hours after local infiltration, 120 hours after interscalene brachial plexus nerve block, 168 hours after sciatic nerve block in the popliteal fossa, and 168 hours after adductor canal block [see Warnings and Precautions (5.2)]. In general, peripheral nerve blocks have shown systemic plasma levels of bupivacaine for extended duration when compared to local infiltration. Systemic plasma levels of bupivacaine following administration of EXPAREL are not correlated with local efficacy.

Absorption

The rate of systemic absorption of bupivacaine is dependent upon the total dose of EXPAREL administered, the route of administration, and the vascularity of the administration site.

Pharmacokinetic parameters of EXPAREL after local infiltration, and following an interscalene brachial plexus nerve block, sciatic nerve block in the popliteal fossa, and adductor canal block were evaluated following surgical procedures. Descriptive statistics of pharmacokinetic parameters of representative EXPAREL doses in each study are provided in Table 5 for adult patients after administration of single doses of EXPAREL via local infiltration; Table 6 for adult patients after administration of single doses of EXPAREL via nerve block; and in Table 7 for pediatric patients aged 6 to less than 17 years old after administration of single doses of EXPAREL via local infiltration.

Table 5: Summary of Pharmacokinetic Parameters for Bupivacaine after Administration of Single Doses of EXPAREL via Local Infiltration in Adult Patients
Parameters [Arithmetic mean (standard deviation) except Tmax where it is median (minimum, maximum).] | Bunionectomy [Patients undergoing bunionectomy (Study 1)] 106 mg (8 mL) | Hemorrhoidectomy [Patients undergoing hemorrhoidectomy (Study 2)] 266 mg (20 mL) | Spine Surgery [Patients undergoing open posterior spinal fusion or reconstructive surgery] 266 mg (20 mL) | Cardiothoracic Surgery [Patients undergoing posterolateral thoracotomy] 266 mg (20 mL)
 | (N=26) | (N=25) | (N=11) | (N=5)
Cmax (ng/mL) | 166 (93) | 867 (353) | 513 (268) | 445 (120)
Tmax (h) | 2 (0.5, 24) | 0.5 (0.25, 36) | 0.6 (0.2, 37) | 0.6 (0.6, 36)
AUC0-40h (h × ng/mL) | NE | NE | 13035 (8782) | 9867 (1332)
AUC(0-last) (h × ng/mL) | 5864 (2038) [AUC0-last, 0-72h;] | 16867 (7868) | 17214 (11621) [AUC0-last, 0-96h] | 14277 (3449)
AUC(inf) (h × ng/mL) | 7105 (2283) | 18289 (7569) | 17917 (12187) | 15768 (4530)
t½ (h) | 34 (17) | 24 (39) | 9 (2) | 14 (6)
NE: Not evaluated

Table 6: Summary of Pharmacokinetic Parameters for Bupivacaine after Administration of Single Doses of EXPAREL via Nerve Block in Adult Patients (Studies 3, 4 and 5)
Parameters [Arithmetic mean (standard deviation) except Tmax where it is median (minimum, maximum).] | Interscalene Brachial Plexus Nerve Block [Patients undergoing total shoulder arthroplasty (Study 3)] | Sciatic Nerve Block in the Popliteal Fossa [Patients undergoing bunionectomy (Study 4)] | Adductor Canal Block [Patients undergoing total knee arthroplasty (Study 5)]
Parameters [Arithmetic mean (standard deviation) except Tmax where it is median (minimum, maximum).] | EXPAREL 133 mg (10 mL) | EXPAREL 133 mg (10 mL) + BUP as Mayo field block (100 mg [100 mg bupivacaine HCl contains 88.6 mg of bupivacaine free base.]) (Total dose: 221.6 mg bupivacaine) | EXPAREL 133 mg (10 mL) + BUP 50 mg + BUP as IPACK (37.5 mg) + BUP (up to 15 mg) as spinal anesthesia (Total dose: 224 mg bupivacaine)
Parameters [Arithmetic mean (standard deviation) except Tmax where it is median (minimum, maximum).] | (N = 12) | (N = 21) | (N = 24)
Cmax (ng/mL) | 207 (137) | 382 (241) | 495 (165)
Tmax (h) | 48 (3, 74) | 8.1 (1.7, 12) | 0.7 (0.4, 72)
AUC(0-last) (h × ng/mL) | 11484 (8615) [AUC0-last, 0-120h ;] | 16005 (6740) [AUC0-last, 0-168h] | 25039 (11921)
AUC(inf) (h × ng/mL) | 11590 (8603) | 17004 (7206) | 25109 (11918)
t½ (h) | 11 (5) | 28 (14) | 11 (3)
BUP: Bupivacaine HCl.
IPACK: Infiltration between the popliteal artery and capsule of the knee
NE: Not evaluated

Table 7: Summary of Pharmacokinetic Parameters for Bupivacaine after Administration of Single Doses of EXPAREL via Local Infiltration in Pediatric Patients Aged 6 to Less Than 17 Years Old (Studies Peds-1 and Peds-2)
Parameters [Arithmetic mean (standard deviation) except Tmax where it is median (minimum, maximum).] | Spine Surgery | Cardiac Surgery
Parameters [Arithmetic mean (standard deviation) except Tmax where it is median (minimum, maximum).] | EXPAREL 4 mg/kg (Maximum 266 mg) | EXPAREL 4 mg/kg (Maximum 266 mg)
Parameters [Arithmetic mean (standard deviation) except Tmax where it is median (minimum, maximum).] | 6 to <17 years (N = 17) | 6 to <12 years (N = 21)
Cmax (ng/mL) | 353 (125) | 447 (243)
Tmax (h) | 1.2 (0.3-26) | 23 (0.2, 55)
AUC(0- 40 h) (h × ng/mL) | 8782 (2834) | 11286 (4791)
AUC(0-last) (h × ng/mL) | NR^1 | 16776 (7936) [AUC0-last, 0-72h]
AUC(inf) (h × ng/mL) | NR^2 | NR^2
t½ (h) | NR^2 | NR^2
NR^1 = Not reported, since the last sampling time point varies among different patients.
NR^2= Not reported, since the terminal elimination phase was not adequately characterized in sufficient number of patients.

Distribution

After bupivacaine has been released from EXPAREL and is absorbed systemically, bupivacaine distribution is expected to be the same as for any bupivacaine HCl solution formulation.

Local anesthetics including bupivacaine are distributed to some extent to all body tissues, with high concentrations found in highly perfused organs such as the liver, lungs, heart, and brain.

Local anesthetics including bupivacaine appear to cross the placenta by passive diffusion. The rate and degree of diffusion is governed by (1) the degree of plasma protein binding, (2) the degree of ionization, and (3) the degree of lipid solubility. Fetal/maternal ratios of local anesthetics appear to be inversely related to the degree of plasma protein binding, because only the free, unbound drug is available for placental transfer. Bupivacaine with a high protein binding capacity (95%) has a low fetal/maternal ratio (0.2 to 0.4). The extent of placental transfer is also determined by the degree of ionization and lipid solubility of the drug. Lipid soluble, non-ionized drugs such as bupivacaine readily enter the fetal blood from the maternal circulation.

Elimination

Metabolism

Amide-type local anesthetics, such as bupivacaine, are metabolized primarily in the liver via conjugation with glucuronic acid. Pipecoloxylidide (PPX) is the major metabolite of bupivacaine; approximately 5% of bupivacaine is converted to PPX. Elimination of drug depends largely upon the availability of plasma protein binding sites in the circulation to carry it to the liver where it is metabolized.

Various pharmacokinetic parameters of the local anesthetics can be significantly altered by the presence of hepatic disease. Patients with hepatic disease, especially those with severe hepatic disease, may be more susceptible to the potential toxicities of the amide-type local anesthetics.

Excretion

After bupivacaine has been released from EXPAREL and is absorbed systemically, bupivacaine excretion is expected to be the same as for other bupivacaine formulations.

The kidney is the main excretory organ for most local anesthetics and their metabolites. Only 6% of bupivacaine is excreted unchanged in the urine.

Urinary excretion is affected by urinary perfusion and factors affecting urinary pH. Acidifying the urine hastens the renal elimination of local anesthetics. Various pharmacokinetic parameters of the local anesthetics can be significantly altered by the presence of renal disease, factors affecting urinary pH, and renal blood flow.

Specific Populations

Hepatic Impairment

Because amide-type local anesthetics, such as bupivacaine, are metabolized by the liver, the effects of decreased hepatic function on bupivacaine pharmacokinetics following administration of EXPAREL were studied in patients with moderate hepatic impairment. Consistent with the hepatic clearance of bupivacaine, mean plasma concentrations were higher in patients with moderate hepatic impairment than in the healthy control volunteers with approximately 1.5- and 1.6-fold increases in the mean values for Cmax and the area under the curve (AUC), respectively. [see Warnings and Precautions (5.1) and Use in Specific Populations (8.6)].

13 NONCLINICAL TOXICOLOGY

13.1 Carcinogenesis, Mutagenesis, Impairment of Fertility

Carcinogenesis

Long-term studies in animals to evaluate the carcinogenic potential of bupivacaine have not been conducted.

Mutagenesis

The mutagenic potential of bupivacaine has not been determined.

Impairment of Fertility

The effect of bupivacaine on fertility has not been determined.

14 CLINICAL STUDIES

14.1 Overview of Clinical Studies in Adult Patients

In five multicenter, randomized, double-blinded, placebo-controlled clinical studies in adults, the efficacy of EXPAREL was established to produce postsurgical:

- Local analgesia via infiltration: One study evaluated the use of EXPAREL in patients undergoing bunionectomy (Study 1); the other study evaluated the use of EXPAREL in patients undergoing hemorrhoidectomy (Study 2) [see Clinical Studies (14.2)].
- Regional analgesia via perineural use: one study (Study 3) evaluated the use of EXPAREL as a brachial plexus nerve block via interscalene or supraclavicular approach in patients undergoing total shoulder arthroplasty (TSA) or rotator cuff repair (RCR) (only two patients had nerve blocks via the supraclavicular approach); one study evaluated the use of EXPAREL as a sciatic nerve block in the popliteal fossa in patients undergoing bunionectomy (Study 4); and one study evaluated the use of EXPAREL as an adductor canal block in patients undergoing total knee arthroplasty (TKA) (Study 5) [see Clinical Studies (14.3)].

Four additional studies (Studies 6, 7, 8, and 9) [see Clinical Studies (14.4)] did not provide sufficient efficacy and/or safety data to support an indication for the following nerve blocks: femoral block in patients undergoing total knee arthroplasty, intercostal nerve block in patients undergoing posterolateral thoracotomy, and combined sciatic (in popliteal fossa) and saphenous (in adductor canal) nerve block [see Indications and Usage (1)].

14.2 Studies in Adults to Produce Postsurgical Local Analgesia

Study 1: Infiltration for Bunionectomy in Adults

A multicenter, randomized, double-blind, placebo-controlled, parallel-group clinical trial (NCT00890682) (Study 1) evaluated the safety and efficacy of 106 mg (8 mL) EXPAREL in 193 adult patients undergoing bunionectomy. The mean age was 43 years (range 18 to 72).

Study medication was administered directly into the site at the conclusion of the surgery, prior to closure. There was an infiltration of placebo or 7 mL of EXPAREL into the tissues surrounding the osteotomy and 1 mL into the subcutaneous tissue.

Pain intensity was rated by the patients on a 0 to 10 numeric rating scale (NRS) out to 72 hours. Postoperatively, patients were allowed rescue medication (5 mg oxycodone/325 mg acetaminophen orally every 4 to 6 hours as needed) or, if that was insufficient within the first 24 hours, ketorolac (15 to 30 mg IV). The primary outcome measure was the area under the curve (AUC) of the NRS pain intensity scores (cumulative pain scores) collected over the first 24-hour period. There was a significant treatment effect for EXPAREL compared to placebo. EXPAREL demonstrated a significant reduction in pain intensity compared to placebo for up to 24 hours. There was no significant difference in the amount of morphine equivalents used through 72 hours post-surgery, 43 mg versus 42 mg for placebo and EXPAREL, respectively. In addition, there was not a significant difference in the percentage of patients that used ketorolac, 43% versus 31% for placebo and EXPAREL, respectively.

Study 2: Infiltration for Hemorrhoidectomy in Adults

A multicenter, randomized, double-blind, placebo-controlled, parallel-group clinical trial (NCT00890721) (Study 2) evaluated the safety and efficacy of 266 mg (20 mL) EXPAREL in 189 adult patients undergoing hemorrhoidectomy. The mean age was 48 years (range 18 to 86).

EXPAREL or placebo were administered directly into the site (greater than or equal to 3 cm) at the conclusion of the surgery. Dilution of 20 mL of EXPAREL with 10 mL of saline, for a total of 30 mL, was divided into six 5-mL aliquots. A field block was performed by visualizing the anal sphincter as a clock face and slowly infiltrating one aliquot to each of the even numbers.

Pain intensity was rated by the patients on a 0 to 10 NRS at multiple time points up to 72 hours. Postoperatively, patients were allowed rescue medication (morphine sulfate 10 mg intramuscular every 4 hours as needed).

The primary outcome measure was the AUC of the NRS pain intensity scores (cumulative pain scores) collected over the first 72-hour period.

There was a significant treatment effect for EXPAREL compared to placebo. See Figure 1 for the mean pain intensity over time for the EXPAREL and placebo treatment groups for the 72-hour efficacy period.

There were statistically significant, but small differences in the amount of opioid rescue analgesia used across the treatment groups, the clinical benefit of which has not been established. The median time to rescue analgesic use was 15 hours for patients treated with EXPAREL and one hour for patients treated with placebo. Twenty-eight percent of patients treated with EXPAREL required no rescue medication at 72 hours compared to 10% treated with placebo. For those patients who did require rescue medication, the mean amount of morphine sulfate intramuscular injections used over 72 hours was 22 mg for patients treated with EXPAREL and 29 mg for patients treated with placebo.

14.3 Nerve Block Studies in Adults to Produce Postsurgical Regional Analgesia

Study 3: Interscalene Brachial Plexus Nerve Block for Total Shoulder Arthroplasty or Rotator Cuff Repair in Adults

A multicenter, randomized, double-blind, placebo-controlled study (NCT02713230) (Study 3) was conducted in 156 adult patients undergoing primary unilateral total shoulder arthroplasty or rotator cuff repair with general anesthesia. The mean age was 61 years (range 33 to 80). Prior to the surgical procedure, patients received 133 mg (10 mL) of EXPAREL expanded with normal saline to 20 mL or placebo as a brachial plexus nerve block (perineural use) via interscalene or supraclavicular approach with ultrasound guidance. Only two patients received nerve block with EXPAREL by supraclavicular approach. Postsurgically, patients were administered acetaminophen/paracetamol up to 1,000 mg orally or intravenously every 8 hours unless contraindicated. Patients were allowed opioid rescue medication administered initially as oral immediate-release oxycodone (initiating at 5-10 mg every 4 hours or as needed). If a patient could not tolerate oral medication, intravenous morphine (2.5-5 mg) or hydromorphone (0.5-1 mg) could be administered every 4 hours or as needed.

In Study 3, there was a statistically significant treatment effect for EXPAREL compared to placebo in cumulative pain scores through 48 hours as measured by the AUC of the visual analog scale (VAS) pain intensity scores. There were statistically significant, but small differences in the amount of opioid consumption through 48 hours, the clinical benefit of which has not been demonstrated. For those patients who required rescue medication, the mean amount of morphine-equivalent opioid rescue used over 48 hours was 12 mg for EXPAREL-treated patients and 54 mg for placebo-treated patients and 23 mg with EXPAREL-treated patients vs. 70 mg for placebo-treated patients over 72 hours.

Although at 48 hours, 9 patients (13%) in the EXPAREL group remained opioid-free compared to 1 patient (1%) in the placebo group, a difference which was statistically significant, at 72 hours, there were 4 (6%) patients in the EXPAREL group who remained opioid-free compared to 1 (1%) patient in the placebo group, a difference that is not statistically significant.

Study 4: Sciatic Nerve Block in the Popliteal Fossa for Bunionectomy in Adults

A multicenter, randomized, double-blind, active controlled study (NCT05157841) (Study 4) was conducted in 185 adult patients undergoing bunionectomy. The mean age was 49 years (range 18 to 76).

Prior to the surgical procedure, patients received 133 mg of EXPAREL mixed with 20 mL saline OR 50 mg (20 mL) of 0.25% bupivacaine HCl mixed with 10 mL saline via sciatic nerve block (perineural use) in the popliteal fossa. All patients received 100 mg (20 mL) of 0.5% immediate-release bupivacaine HCl as a Mayo field block after study drug administration (i.e., in the operating room immediately prior to surgical incision). All patients also received a dose of 1,000 mg of intravenous (IV) acetaminophen at the time of surgical incision. IV fentanyl was allowed for intraoperative pain control (not exceeding 1 mcg/kg unless deemed medically necessary).

Postsurgically, all patients received one post-operative dose of 1,000 mg IV acetaminophen, administered approximately 8 hours after the first dose (approximately 8 hours after incision). Patients were administered pain medications on an as needed basis; opioids were not given on a pre-determined schedule. Patients were allowed opioid rescue medication administered initially as oral immediate-release oxycodone (initiating at 5 mg and increasing the dose to 10 mg if initial opioid dose was insufficient). If a patient could not tolerate oral medication or the oral oxycodone pain relief was insufficient, IV morphine (initiated at 2 mg) or hydromorphone (initiated at 0.2 mg) could be administered. No NSAIDs or other opioids including tramadol were allowed for the breakthrough pain management and no acetaminophen (other than the scheduled IV acetaminophen) was used for breakthrough pain.

In Study 4, there was a statistically significant treatment effect for EXPAREL (with 0.5% immediate-release bupivacaine HCl as a Mayo field block) compared to bupivacaine HCl (with 0.5% immediate-release bupivacaine HCl as a Mayo field block) in cumulative pain scores through 96 hours as measured by AUC of the NRS pain intensity scores. There were statistically significant differences in the total amount of postsurgical opioid medication used through 96 hours, the clinical benefit of which has not been demonstrated. For those patients who required postsurgical opioid medication, the mean amount of morphine-equivalent opioid rescue used over 96 hours was 18 mg for patients treated with EXPAREL + Mayo field block and 45 mg for patients treated with bupivacaine HCl + Mayo field block. There was also a statistically significant difference in the percentage of opioid-free patients through 96 hours compared with bupivacaine HCl (24% in the EXPAREL + Mayo field block vs. 6% in the bupivacaine HCl + Mayo field block).

See Figure 2 for the LS mean pain intensity scores after administration of either 133 mg of EXPAREL or 50 mg of 0.25% bupivacaine HCl.

Figure 2. NRS Pain Intensity After Administration of Study Drug by Sciatic Nerve Block in the Popliteal Fossa.

Study 5: Adductor Canal Block for Total Knee Arthroplasty in Adults

A multicenter, randomized, double-blind, active controlled study (NCT05139030) (Study 5) was conducted in 166 adult patients undergoing primary unilateral total knee arthroplasty. The mean age was 62 years (range 37 to 83).

Prior to the surgical procedure, patients received (via adductor canal block) (perineural use):

- 133 mg (10 mL) of 1.3% EXPAREL admixed with 50 mg (10 mL) of 0.5% bupivacaine HCl or
- 50 mg (10 mL) of 0.5% bupivacaine HCl mixed with 10 mL normal saline.

All patients also received 37.5 mg (15 mL) of 0.25% immediate-release bupivacaine HCl as an infiltration between the popliteal artery and capsule of the knee (IPACK) block immediately following study drug administration. All patients received spinal anesthesia immediately prior to surgery with 0.5% bupivacaine HCl (up to 15 mg). All patients also received a dose of 1,000 mg of intravenous (IV) acetaminophen at the time of surgical incision. IV fentanyl was allowed for intraoperative pain control (not exceeding 1 ug/kg unless deemed medically necessary).

Postsurgically, all patients received one post-operative dose of 1,000 mg IV acetaminophen, administered approximately 8 hours after the first dose (approximately 8 hours after incision). Patients were administered pain medications on an as needed basis for breakthrough pain; opioids were not given on a pre-determined schedule. Patients were allowed opioid rescue medication administered initially as oral immediate-release oxycodone (initiating at 5 mg and increasing the dose to 10 mg if initial opioid dose was insufficient). If a patient could not tolerate oral medication or the oral oxycodone pain relief was insufficient, IV morphine (initiated at 2 mg) or hydromorphone (initiated at 0.2 mg) could be administered. No NSAIDs or other opioids including tramadol were allowed for the breakthrough pain management and no acetaminophen (other than the scheduled IV acetaminophen) was used for breakthrough pain.

In Study 5, there was a statistically significant treatment effect for EXPAREL + IPACK block compared to bupivacaine HCl + IPACK in cumulative pain scores through 96 hours as measured by AUC of the NRS pain intensity scores. There were statistically significant differences in the total amount of postsurgical opioid medication used through 96 hours, the clinical benefit of which has not been demonstrated. For those patients who required postsurgical opioid medication, the mean amount of morphine-equivalent opioid rescue used over 96 hours was 102 mg for patients treated with EXPAREL + IPACK and 133 mg for patients treated with bupivacaine HCl+ IPACK. The median time to first postsurgical use was 4.2 hours for patients treated with EXPAREL + IPACK and 3.6 hours for patients treated with bupivacaine HCl + IPACK.

See Figure 3 for LS mean pain intensity scores after administration of either 133 mg of 1.3% EXPAREL admixed with 50 mg) of 0.5% bupivacaine HCl or 50 mg of 0.5% bupivacaine HCl.

Figure 3. NRS Pain Intensity After Administration of Study Drug by Adductor Canal Block

14.4 Studies That Do Not Support an Indication for Certain Nerve Blocks in Adults

Studies 6 and 7: Inadequate Demonstration of Efficacy and Safety in Femoral Nerve Block in Total Knee Arthroplasty

EXPAREL was administered via a femoral nerve block in two placebo-controlled studies in adults (Studies 6 and 7). The results of these studies did not support a femoral nerve block indication due to inadequate safety data (Study 6) and/or due to inadequate efficacy findings (Study 7). In addition, patient falls were reported only in the EXPAREL treatment groups, and none was reported in placebo groups.

Study 6

Study 6, a multicenter, randomized, double-blind, parallel-group, placebo-controlled study (NCT01683071), was conducted in 196 adult patients undergoing primary unilateral total knee arthroplasty (TKA) under general or spinal anesthesia. The mean age was 65 years (range 42 to 88). Prior to the surgical procedure, 266 mg (20 mL) of EXPAREL or placebo was administered as a femoral nerve block with ultrasound guidance. Postsurgically, patients were allowed opioid rescue medication administered initially by intravenous injection of hydromorphone and subsequently by a patient-controlled analgesia (PCA) pump containing morphine or hydromorphone only. Once patients were tolerating oral medication, oral immediate-release oxycodone was administered on an as-needed basis (but not more than 10 mg every 4 hours) or, if that was insufficient, a third rescue of 1.25 mg/mL of 0.125% bupivacaine HCl was administered at a rate of 8 mL per hour via the previously placed femoral nerve catheter.

In this study, there was a statistically significant treatment effect for EXPAREL compared to placebo in cumulative pain scores through 72 hours as measured by the AUC of the NRS pain (at rest) intensity scores.

There was a statistically significant, although small decrease in opioid consumption for the EXPAREL treatment group compared to the placebo group, the clinical benefit of which has not been established. All patients in both the EXPAREL and placebo treatment groups required opioid rescue medication during the first 72 hours. The mean amount of opioid rescue used over 72 hours was 76 mg for patients treated with EXPAREL and 103 mg for patients treated with placebo.

The study was inadequate to fully characterize the safety of EXPAREL when used for femoral nerve block due to patient falls, which occurred only in the EXPAREL-treated patients and not in the placebo-treated patients.

Study 7

Study 7, a multicenter, randomized, double-blind, parallel-group, placebo-controlled study (NCT02713178), was conducted in 230 adult patients undergoing primary unilateral total knee arthroplasty (TKA) under general or spinal anesthesia. The mean age was 65 years (range 39 to 89). Prior to the surgical procedure, either 266 mg (20 mL) of EXPAREL or 133 mg (10 mL) of EXPAREL plus 10 mL of normal saline or placebo was administered as a femoral nerve block with ultrasound guidance. In addition to study drug, 8 mL of 0.5% bupivacaine HCl diluted with 8 mL of normal saline was administered by the surgeon as a periarticular infiltration to the posterior capsule (8 mL each behind the medial and lateral condyles) before placement of the prosthesis. Postsurgically, patients were allowed opioid rescue medication consisting of oral immediate-release oxycodone (initiated at 5 to 10 mg every 4 hours or as needed). If a patient could not tolerate oral medication, IV morphine (2.5 to 5 mg) or hydromorphone (0.5 to 1 mg) was permitted every 4 hours or as needed. Patient-controlled analgesia was not permitted. No other analgesic agents, including NSAIDs, were permitted through 108 hours. However, to reflect the current standard of care of postsurgical multimodal therapy, all patients received cyclobenzaprine (a single dose of 10 mg orally or as needed) and acetaminophen/paracetamol (up to 1,000 mg orally or IV every 8 hours for a maximum total daily dose of 3000 mg) postsurgically.

In this study there were no statistically significant treatment effects for the EXPAREL group compared to the placebo group in cumulative pain intensity scores or total opioid consumption. All patients in the EXPAREL and placebo treatment groups required opioid rescue medication over 72 hours. The median Tmax of bupivacaine observed in this study was 72 hours with a range of 2.5 to 108 hours. Similar to Study 6, patient falls only occurred in the EXPAREL-treated patients and not the placebo-treated patients.

Study 8: Lack of Efficacy in Intercostal Nerve Block for Posterolateral Thoracotomy

A multicenter, randomized, double-blind, placebo-controlled study was conducted in 191 adult patients undergoing posterolateral thoracotomy under general anesthesia (NCT01802411) (Study 8). The mean age was 58 years (range 18 to 82).

After the surgical procedure was completed but prior to the surgical site closure, 266 mg (20 mL) of EXPAREL was administered by the surgeon as an intercostal nerve block divided into three equal doses in three syringes of approximately 88 mg in 6.6 mL volume per nerve, and administered to each of three nerve segments (index nerve, nerve above, and nerve below). Postsurgically, patients were allowed opioid rescue medication administered initially by intravenous fentanyl 100 mcg, which was to be administered once via bolus only. For the US sites, the second rescue medication was to be PCA-administered morphine or hydromorphone. For the European sites, the second rescue medication was to be intramuscular administered morphine up to 10 mg every 4 hours. At all sites, once a patient was tolerating oral medication, oral immediate-release oxycodone was administered (but not more than 10 mg every 4 hours). Patients who did not achieve adequate pain relief with this regimen were to be withdrawn from the study and followed for safety only.

In this study there were no statistically significant treatment effects for EXPAREL 266 mg compared to placebo in cumulative pain intensity scores or total opioid consumption. Four percent of patients treated with EXPAREL required no rescue medication at 72 hours compared to 1% treated with placebo. For those patients who did require rescue medication, the mean amount of opioid rescue used over 72 hours was 71 mg for patients treated with EXPAREL and 71 mg for patients treated with placebo. The median Tmax of bupivacaine observed in this study was 1 hour with a range of 0.5 hours to 50 hours.

Study 9: Lack of Efficacy in Combined Sciatic (in popliteal fossa) and Saphenous (in adductor canal) Nerve Block Study in Lower Extremity Surgeries

A multicenter, randomized, double-blind, active-controlled trial (NCT04518462) (Study 9) was conducted in 119 adult patients who underwent foot and ankle procedures (bunionectomy, first metatarsophalangeal fusion, forefoot & hindfoot fusion, total ankle arthroplasty). The mean age was 48 years (range 20 to 72). Prior to the surgical procedure, patients received one of the following three treatments under ultrasound guidance as a sciatic nerve block in the popliteal fossa and a saphenous nerve block in the adductor canal:

- 266 mg of EXPAREL (20 mL) admixed with 20 mL of 0.9% Sodium Chloride Injection (referred to as normal saline (NS)),
- 266 mg of EXPAREL (20 mL) admixed with 50 mg of 0.25% bupivacaine HCl (20 mL), or
- 100 mg of 0.25% bupivacaine (40 mL).

The total volume (40 mL) was divided evenly between the two blocks. All patients received general anesthesia or nonopioid sedation (except fentanyl); were allowed medication for intraoperative nausea/vomiting prevention; and were allowed medication for breakthrough pain postsurgery which followed a step-wise approach starting with acetaminophen or a nonsteroidal anti-inflammatory drug (not exceeding the maximum dose), and, if needed escalating to an initial 5 mg dose of oxycodone, then to a 10 mg dose of oxycodone, and finally to intravenous morphine (initiated at 2 mg) or intravenous hydromorphone (initiated at 0.2 mg).

In Study 9 there was no significant difference in the primary endpoint [least square mean (LSM) area under the curve (AUC) numerical rating scale (NRS) pain score from 0 to 96 hours after surgery] between EXPAREL + NS and the 0.25% bupivacaine HCl treatment groups. Cumulative opioid consumption differences between groups were nonsignificant 0-96 hours after surgery. The LSM amount of opioids received over 96 hours was 21 mg in EXPAREL group and 20 mg in bupivacaine HCl group.

16 HOW SUPPLIED/STORAGE AND HANDLING

EXPAREL (bupivacaine liposome injectable suspension) is a white to off-white milky aqueous suspension that is available in the following single-dose vials.

1.3% (266 mg/20 mL) (13.3 mg/mL) single-dose vial, (NDC 65250-266-20) packaged in cartons of 10 (NDC 65250-266-09) and cartons of 4 (NDC 65250-266-04)
1.3% (133 mg/10 mL) (13.3 mg/mL) single-dose vial, (NDC 65250-133-10) packaged in cartons of 10 (NDC-65250-133-09) and cartons of 4 (NDC 65250-133-04)

Storage

Store EXPAREL vials refrigerated between 2°C to 8°C (36°F to 46°F). EXPAREL may be held at a controlled room temperature of 20°C to 25°C (68°F to 77°F) for up to 30 days in sealed, intact (unopened) vials. Do not re-refrigerate vials.

Do not freeze or expose EXPAREL to high temperatures (greater than 40°C or 104°F) for an extended period. Do not administer EXPAREL if it is suspected of having been frozen or exposed to high temperatures. Do not use the vial if the stopper is bulging.

Handling

See Dosage and Administration (2.1, 2.4) for important preparation instructions.

17 PATIENT COUNSELING INFORMATION

Inform patients that use of local anesthetics may cause methemoglobinemia, a serious condition that must be treated promptly. Advise patients or caregivers to seek immediate medical attention if they or someone in their care experience the following signs or symptoms: pale, gray, or blue colored skin (cyanosis); headache; rapid heart rate; shortness of breath; lightheadedness; or fatigue.

Inform patients in advance that EXPAREL can cause temporary loss of sensation or motor activity that may last for up to 5 days.

Manufactured for Pacira Pharmaceuticals, Inc., a wholly owned subsidiary of Pacira BioSciences, Inc.
San Diego, CA 92121 USA

Trademark of Pacira Pharmaceuticals, Inc.

©2023 Pacira Pharmaceuticals, Inc. All rights reserved.

For additional information call 1-855-RX-EXPAREL (1-855-793-9727) or visit www.EXPAREL.com

PRINCIPAL DISPLAY PANEL - 133 mg/10 mL Vial Label

NDC 65250-133-10

EXPAREL®
(bupivacaine liposome injectable suspension)

STERILE
1.3%
Rx Only

133 mg / 10 mL (13.3 mg/mL)

For infiltration, interscalene brachial plexus
nerve block, sciatic nerve block in the
popliteal fossa, and adductor canal block

10 mL vial

PRINCIPAL DISPLAY PANEL - 133 mg/10 mL Vial Carton - NDC 65250-133-09

NDC 65250-133-09
Contains 10
10 mL Vials

EXPAREL®
(bupivacaine liposome injectable suspension)

1.3%
133 mg/10 mL (13.3 mg/mL)

Rx Only

For infiltration, interscalene brachial plexus nerve block, sciatic nerve block
in the popliteal fossa, and adductor canal block

Contents: Each 10 mL vial contains 133 mg of bupivacaine free base.

Usual Dosage: see Prescribing Information. Do not substitute for or with other
formulations containing bupivacaine or bupivacaine HCl. Single dose vial;
discard any unused portion.

Do not freeze. Do not use the vial if the stopper is bulging.

PRINCIPAL DISPLAY PANEL - 133 mg/10 mL Vial Carton - NDC 65250-133-04

NDC 65250-133-04
Contains 4
10 mL Vials

EXPAREL®
(bupivacaine liposome injectable suspension)

1.3%
133 mg/10 mL (13.3 mg/mL)

Rx Only

For infiltration, interscalene brachial plexus nerve block, sciatic nerve block
in the popliteal fossa, and adductor canal block

Contents: Each 10 mL vial contains 133 mg of bupivacaine free base.

Usual Dosage: see Prescribing Information. Do not substitute for or with other
formulations containing bupivacaine or bupivacaine HCl. Single dose vial;
discard any unused portion.

Do not freeze. Do not use the vial if the stopper is bulging.

PRINCIPAL DISPLAY PANEL - 266 mg/20 mL Vial Label

NDC 65250-266-20

EXPAREL®
(bupivacaine liposome injectable suspension)

STERILE
1.3%
Rx Only

266 mg/20 mL (13.3 mg/mL)

For infiltration, interscalene brachial plexus
nerve block, sciatic nerve block in the
popliteal fossa, and adductor canal block

20 mL Vial

PRINCIPAL DISPLAY PANEL - 266 mg/20 mL Vial Carton - NDC 65250-266-09

NDC 65250-266-09
Contains 10
20 mL Vials

EXPAREL®
(bupivacaine liposome injectable suspension)

1.3%
266 mg/20 mL (13.3 mg/mL)

Rx Only

For infiltration, interscalene brachial plexus nerve block, sciatic nerve block
in the popliteal fossa, and adductor canal block

Contents: Each 20 mL vial contains 266 mg of bupivacaine free base.

Usual Dosage: see Prescribing Information. Do not substitute for or with other
formulations containing bupivacaine or bupivacaine HCl. Single dose vial;
discard any unused portion.

Do not freeze. Do not use the vial if the stopper is bulging.

PRINCIPAL DISPLAY PANEL - 266 mg/20 mL Vial Carton - NDC 65250-266-04

NDC 65250-266-04
Contains 4
20 mL Vials

EXPAREL®
(bupivacaine liposome injectable suspension)

1.3%
266 mg/20 mL (13.3 mg/mL)

Rx Only

For infiltration, interscalene brachial plexus nerve block, sciatic nerve block
in the popliteal fossa, and adductor canal block

Contents: Each 20 mL vial contains 266 mg of bupivacaine free base.

Usual Dosage: see Prescribing Information. Do not substitute for or with other
formulations containing bupivacaine or bupivacaine HCl. Single dose vial;
discard any unused portion.

Do not freeze. Do not use the vial if the stopper is bulging.